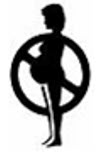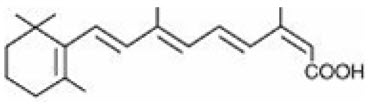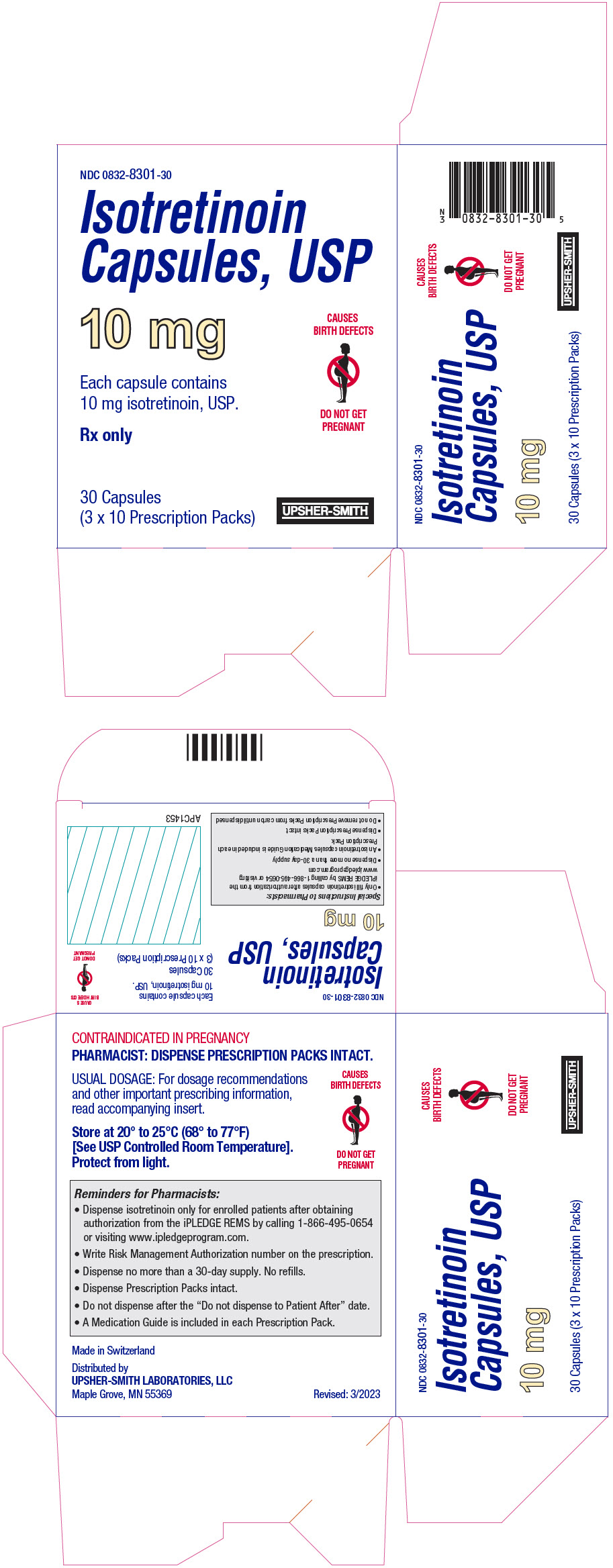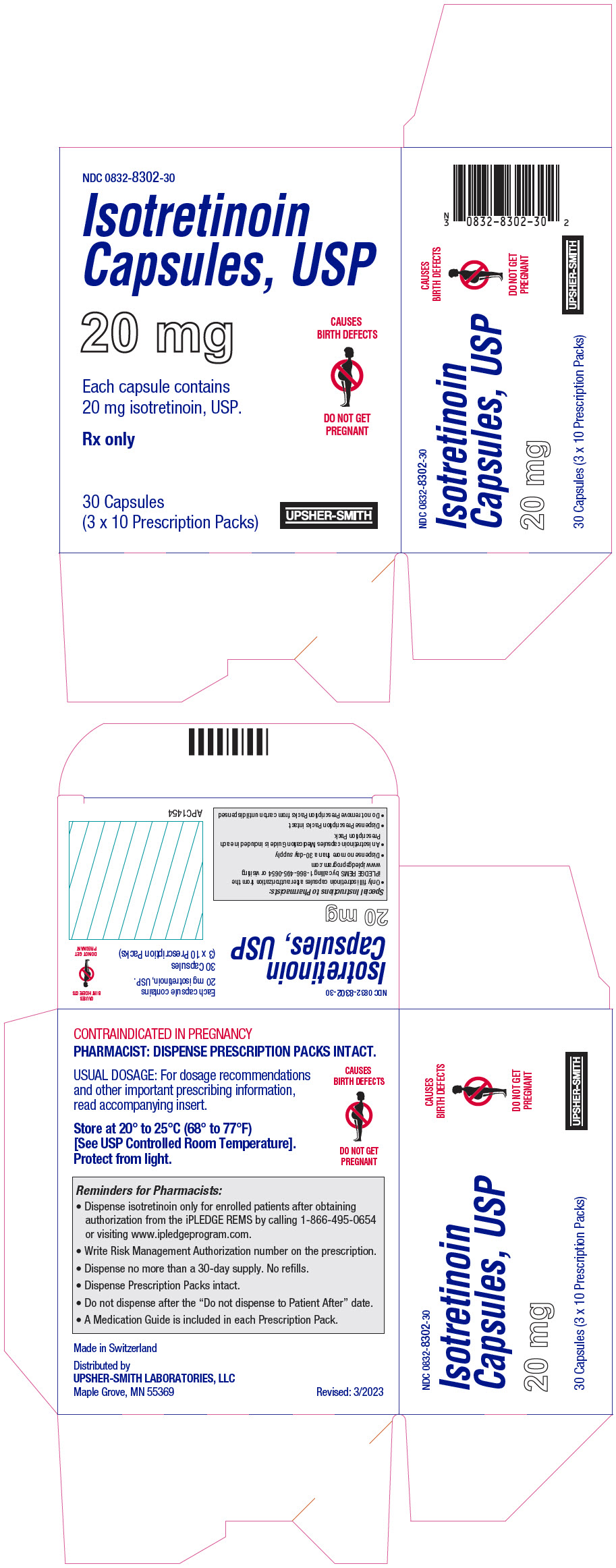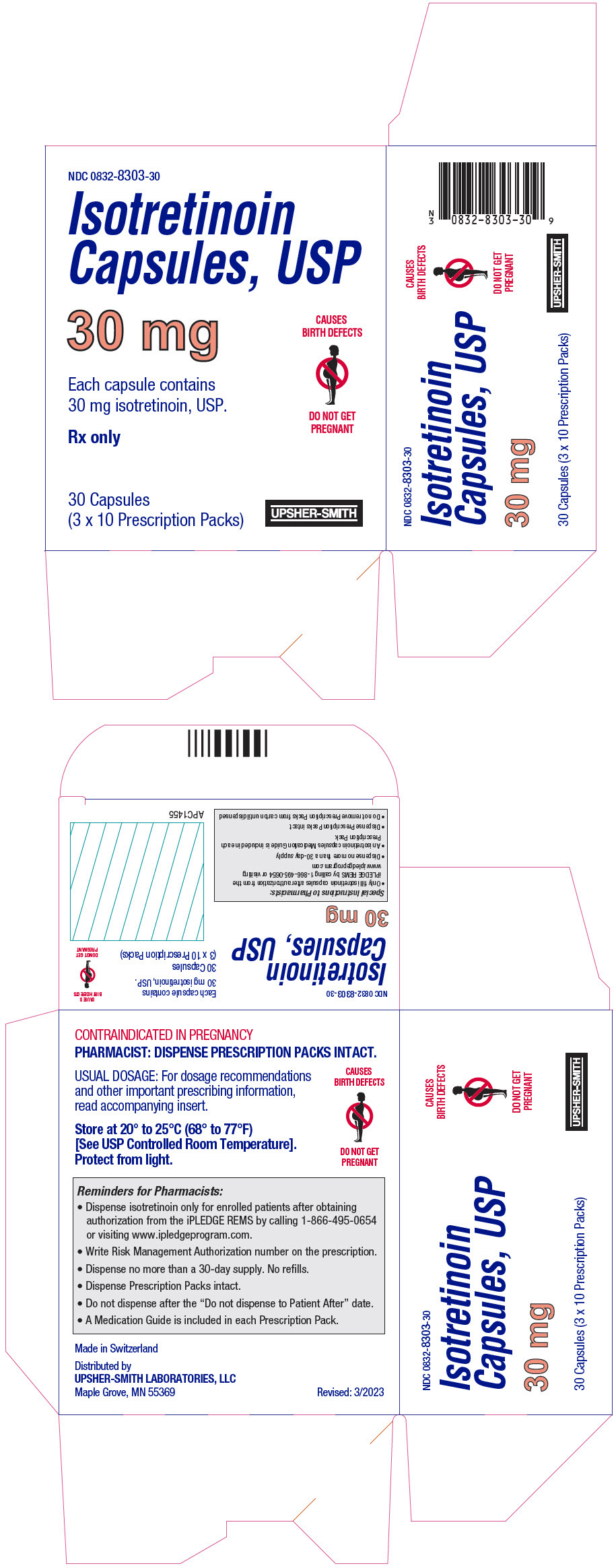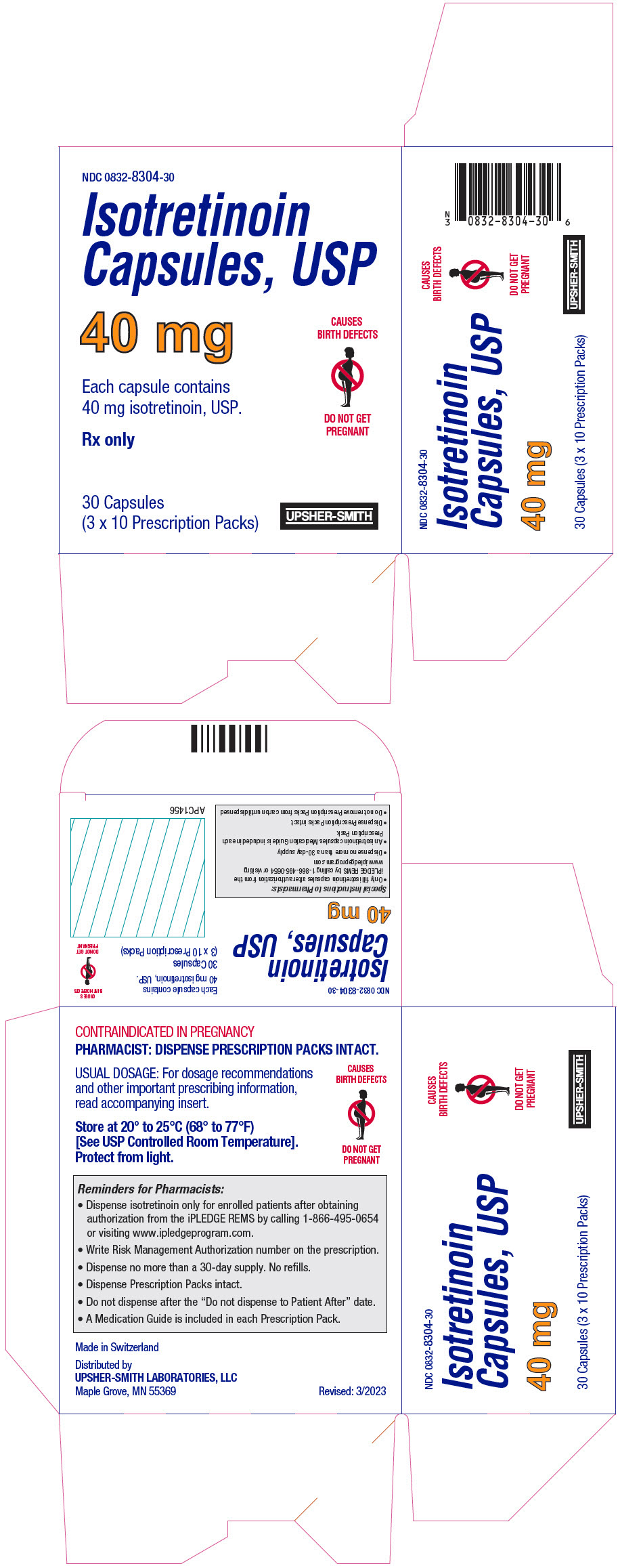 DRUG LABEL: Isotretinoin
NDC: 0832-8301 | Form: CAPSULE, LIQUID FILLED
Manufacturer: Upsher-Smith Laboratories, LLC
Category: prescription | Type: HUMAN PRESCRIPTION DRUG LABEL
Date: 20260213

ACTIVE INGREDIENTS: ISOTRETINOIN 10 mg/1 1
INACTIVE INGREDIENTS: YELLOW WAX; BUTYLATED HYDROXYANISOLE; EDETATE DISODIUM; HYDROGENATED SOYBEAN OIL; .ALPHA.-TOCOPHEROL, DL-; SOYBEAN OIL; GELATIN, UNSPECIFIED; GLYCERIN; SORBITOL; SHELLAC; ALCOHOL; ISOPROPYL ALCOHOL; FERROSOFERRIC OXIDE; BUTYL ALCOHOL; PROPYLENE GLYCOL; AMMONIA; TITANIUM DIOXIDE; FERRIC OXIDE YELLOW

Isotretinoin Capsules, USP 10 mg, 20 mg, 30 mg, 40 mg

Rx only

CAUSES BIRTH DEFECTS

DO NOT GET PREGNANT

BOXED WARNING

CONTRAINDICATIONS AND WARNINGS

Isotretinoin capsules must not be used by patients who are or may become pregnant. There is an extremely high risk that life-threatening birth defects will result if pregnancy occurs while taking isotretinoin capsules in any amount, even for short periods of time. Potentially any fetus exposed during pregnancy can be affected. There are no accurate means of determining whether an exposed fetus has been affected.

Birth defects which have been documented following isotretinoin capsules exposure include abnormalities of the face, eyes, ears, skull, central nervous system, cardiovascular system, and thymus and parathyroid glands. Cases of IQ scores less than 85 with or without other abnormalities have been reported. There is an increased risk of spontaneous abortion, and premature births have been reported.

Documented external abnormalities include: skull abnormality; ear abnormalities (including anotia, micropinna, small or absent external auditory canals); eye abnormalities (including microphthalmia); facial dysmorphia; cleft palate. Documented internal abnormalities include: CNS abnormalities (including cerebral abnormalities, cerebellar malformation, hydrocephalus, microcephaly, cranial nerve deficit); cardiovascular abnormalities; thymus gland abnormality; parathyroid hormone deficiency. In some cases death has occurred with certain of the abnormalities previously noted.

If pregnancy does occur during treatment of a patient who is taking isotretinoin capsules, isotretinoin capsules must be discontinued immediately and the patient should be referred to an Obstetrician-Gynecologist experienced in reproductive toxicity for further evaluation and counseling.

Special Prescribing Requirements

Because of isotretinoin teratogenicity and to minimize fetal exposure, isotretinoin capsules approved for marketing only under a special restricted distribution program approved by the Food and Drug Administration. This REMS is called iPLEDGE®. Isotretinoin capsules must only be prescribed by prescribers who are enrolled and activated with the iPLEDGE REMS. Isotretinoin capsule smust only be dispensed by a pharmacy enrolled and activated with iPLEDGE, and must only be dispensed to patients who are enrolled andmeet all the requirements of iPLEDGE (see PRECAUTIONS).

Table 1 Monthly Required iPLEDGE Interactions
 | Patients Who Can Become Pregnant | Patients Who Cannot Become Pregnant
PRESCRIBER
Confirms patient counseling | X | X
Enters the 2 contraception forms chosen by the patient | X
Enters pregnancy test results | X
PATIENT
Answers educational questions before every prescription | X
Enters 2 forms of contraception | X
PHARMACIST
Contacts system to get an authorization | X | X

DESCRIPTION

Isotretinoin, a retinoid, is available as isotretinoin capsules in 10-mg, 20-mg, 30-mg and 40-mg soft gelatin capsules for oral administration. Each capsule contains yellow wax, butylated hydroxyanisole, edetate disodium, hydrogenated vegetable oil, tocopherol, and soybean oil. Gelatin capsules contain gelatin, glycerin and non-crystallizing sorbitol solution, with the following dye systems: 10 mg - ferric oxide (yellow) and titanium dioxide; 20 mg - titanium dioxide; 30 mg - titanium dioxide and ferric oxide (red); 40 mg - FD&C Yellow No. 6 and titanium dioxide.

The edible imprinting ink for all the capsules contains: shellac glaze, dehydrated alcohol, isopropyl alcohol, iron oxide black, N-butyl alcohol, propylene glycol, and ammonium hydroxide.

Meets USP Dissolution Test 6.

Chemically, isotretinoin is 13- cis-retinoic acid and is related to both retinoic acid and retinol (vitamin A). It is a yellow to orange crystalline powder with a molecular weight of 300.44. The structural formula is:

CLINICAL PHARMACOLOGY

Isotretinoin is a retinoid, which when administered in pharmacologic dosages of 0.5 to 1 mg/kg/day (see DOSAGE AND ADMINISTRATION), inhibits sebaceous gland function and keratinization. The exact mechanism of action of isotretinoin is unknown.

Nodular Acne

Clinical improvement in nodular acne patients occurs in association with a reduction in sebum secretion. The decrease in sebum secretion is temporary and is related to the dose and duration of treatment with isotretinoin capsules, and reflects a reduction in sebaceous gland size and an inhibition of sebaceous gland differentiation.^1

Pharmacokinetics

Absorption

Due to its high lipophilicity, oral absorption of isotretinoin is enhanced when given with a high-fat meal. In a crossover study, 74 healthy adult subjects received a single 80 mg oral dose (2 × 40 mg capsules) of isotretinoin under fasted and fed conditions. Both peak plasma concentration (Cmax) and the total exposure (AUC) of isotretinoin were more than doubled following a standardized high-fat meal when compared with isotretinoin given under fasted conditions (see Table 2). The observed elimination half-life was unchanged. This lack of change in half-life suggests that food increases the bioavailability of isotretinoin without altering its disposition. The time to peak concentration (Tmax) was also increased with food and may be related to a longer absorption phase. Therefore, isotretinoin should always be taken with food (see DOSAGE AND ADMINISTRATION). Clinical studies have shown that there is no difference in the pharmacokinetics of isotretinoin between patients with nodular acne and healthy subjects with normal skin.

Table 2 Pharmacokinetic Parameters of Isotretinoin Mean (%CV), N=74
Isotretinoin 2×40 mg Capsules | AUC0–∞ (ng∙hr/mL) | Cmax (ng/mL) | Tmax (hr) | t1/2 (hr)
Fed [Eating a standardized high-fat meal.] | 10,004 (22%) | 862 (22%) | 5.3 (77%) | 21 (39%)
Fasted | 3,703 (46%) | 301 (63%) | 3.2 (56%) | 21 (30%)

Distribution

Isotretinoin is more than 99.9% bound to plasma proteins, primarily albumin.

Metabolism

Following oral administration of isotretinoin, at least three metabolites have been identified in human plasma: 4- oxo-isotretinoin, retinoic acid (tretinoin), and 4- oxo-retinoic acid (4- oxo-tretinoin). Retinoic acid and 13- cis-retinoic acid are geometric isomers and show reversible interconversion. The administration of one isomer will give rise to the other. Isotretinoin is also irreversibly oxidized to 4- oxo-isotretinoin, which forms its geometric isomer 4- oxo-tretinoin.

After a single 80 mg oral dose of isotretinoin to 74 healthy adult subjects, concurrent administration of food increased the extent of formation of all metabolites in plasma when compared to the extent of formation under fasted conditions.

All of these metabolites possess retinoid activity that is in some in vitro models more than that of the parent isotretinoin. However, the clinical significance of these models is unknown. After multiple oral dose administration of isotretinoin to adult cystic acne patients (≥18 years), the exposure of patients to 4-oxo-isotretinoin at steady-state under fasted and fed conditions was approximately 3.4 times higher than that of isotretinoin.

In vitro studies indicate that the primary P450 isoforms involved in isotretinoin metabolism are 2C8, 2C9, 3A4, and 2B6. Isotretinoin and its metabolites are further metabolized into conjugates, which are then excreted in urine and feces.

Elimination

Following oral administration of an 80 mg dose of^14C-isotretinoin as a liquid suspension,^14C-activity in blood declined with a half-life of 90 hours. The metabolites of isotretinoin and any conjugates are ultimately excreted in the feces and urine in relatively equal amounts (total of 65% to 83%). After a single 80 mg oral dose of isotretinoin to 74 healthy adult subjects under fed conditions, the mean ±SD elimination half-lives (t1/2) of isotretinoin and 4- oxo-isotretinoin were 21 ± 8.2 hours and 24 ± 5.3 hours, respectively. After both single and multiple doses, the observed accumulation ratios of isotretinoin ranged from 0.9 to 5.43 in patients with cystic acne.

Special Patient Populations

Pediatric Patients

The pharmacokinetics of isotretinoin were evaluated after single and multiple doses in 38 pediatric patients (12 to 15 years) and 19 adult patients (≥18 years) who received isotretinoin for the treatment of severe recalcitrant nodular acne. In both age groups, 4- oxo-isotretinoin was the major metabolite; tretinoin and 4- oxo-tretinoin were also observed. The dose-normalized pharmacokinetic parameters for isotretinoin following single and multiple doses are summarized in Table 3for pediatric patients. There were no statistically significant differences in the pharmacokinetics of isotretinoin between pediatric and adult patients.

Table 3 Pharmacokinetic Parameters of Isotretinoin Following Single and Multiple Dose Administration in Pediatric Patients, 12 to 15 Years of Age Mean (± SD), N=38 [The single and multiple dose data in this table were obtained following a non-standardized meal that is not comparable to the high-fat meal that was used in the study in Table 2.]
Parameter | Isotretinoin (Single Dose) | Isotretinoin (Steady-State)
Cmax(ng/mL) | 573.25 (278.79) | 731.98 (361.86)
AUC(0–12)(ng∙hr/mL) | 3,033.37 (1,394.17) | 5,082 (2,184.23)
AUC(0–24)(ng∙hr/mL) | 6,003.81 (2,885.67) | –
Tmax(hr) [Median (range)] | 6 (1–24.6) | 4 (0–12)
Cssmin(ng/mL) | – | 352.32 (184.44)
T1/2(hr) | – | 15.69 (5.12)
CL/F (L/hr) | – | 17.96 (6.27)

In pediatric patients (12 to 15 years), the mean ± SD elimination half-lives (t1/2)of isotretinoin and 4- oxo-isotretinoin were 15.7 ± 5.1 hours and 23.1 ± 5.7 hours, respectively. The accumulation ratios of isotretinoin ranged from 0.46 to 3.65 for pediatric patients.

INDICATIONS AND USAGE

Severe Recalcitrant Nodular Acne

Isotretinoin capsules are indicated for the treatment of severe recalcitrant nodular acne. Nodules are inflammatory lesions with a diameter of 5 mm or greater. The nodules may become suppurative or hemorrhagic. "Severe," by definition,^2means "many" as opposed to "few or several" nodules. Because of significant adverse effects associated with its use, isotretinoin capsules should be reserved for patients with severe nodular acne who are unresponsive to conventional therapy, including systemic antibiotics.In addition, isotretinoin capsules are indicated only for those patients who are not pregnant, because isotretinoin capsules can cause life-threatening birth defects (see Boxed CONTRAINDICATIONS AND WARNINGS).

A single course of therapy for 15 to 20 weeks has been shown to result in complete and prolonged remission of disease in many patients.^1,3,4If a second course of therapy is needed, it should not be initiated until at least 8 weeks after completion of the first course, because experience has shown that patients may continue to improve while off isotretinoin capsules. The optimal interval before retreatment has not been defined for patients who have not completed skeletal growth (see WARNINGS: Skeletal: Bone Mineral Density, Hyperostosis, Premature Epiphyseal Closure).

CONTRAINDICATIONS

Pregnancy

Category X

See Boxed CONTRAINDICATIONS AND WARNINGS.

Allergic Reactions

Isotretinoin capsules are contraindicated in patients who are hypersensitive to this medication or to any of its components (see PRECAUTIONS: Hypersensitivity).

WARNINGS

Psychiatric Disorders

Isotretinoin capsules may cause depression, psychosis and, rarely, suicidal ideation, suicide attempts, suicide, and aggressive and/or violent behaviors. No mechanism of action has been established for these events (see ADVERSE REACTIONS: Psychiatric). Prescribers should read the brochure, Recognizing Psychiatric Disorders in Adolescents and Young Adults: A Guide for Prescribers of Isotretinoin.Prescribers should be alert to the warning signs of psychiatric disorders to guide patients to receive the help they need. Therefore, prior to initiation of isotretinoin capsules therapy, patients and family members should be asked about any history of psychiatric disorder, and at each visit during therapy patients should be assessed for symptoms of depression, mood disturbance, psychosis, or aggression to determine if further evaluation may be necessary. Signs and symptoms of depression, as described in the brochure ("Recognizing Psychiatric Disorders in Adolescents and Young Adults"), include sad mood, hopelessness, feelings of guilt, worthlessness or helplessness, loss of pleasure or interest in activities, fatigue, difficulty concentrating, change in sleep pattern, change in weight or appetite, suicidal thoughts or attempts, restlessness, irritability, acting on dangerous impulses, and persistent physical symptoms unresponsive to treatment. Patients should stop isotretinoin capsules and the patient or a family member should promptly contact their prescriber if the patient develops depression, mood disturbance, psychosis, or aggression, without waiting until the next visit. Discontinuation of isotretinoin capsules therapy may be insufficient; further evaluation may be necessary. While such monitoring may be helpful, it may not detect all patients at risk. Patients may report mental health problems or family history of psychiatric disorders. These reports should be discussed with the patient and/or the patient's family. A referral to a mental health professional may be necessary. The physician should consider whether isotretinoin capsules therapy is appropriate in this setting; for some patients the risks may outweigh the benefits of isotretinoin capsules therapy.

Pseudotumor Cerebri

Isotretinoin capsules use has been associated with a number of cases of pseudotumor cerebri (benign intracranial hypertension), some of which involved concomitant use of tetracyclines. Concomitant treatment with tetracyclines should therefore be avoided. Early signs and symptoms of pseudotumor cerebri include papilledema, headache, nausea and vomiting, and visual disturbances. Patients with these symptoms should be screened for papilledema and, if present, they should be told to discontinue isotretinoin capsules immediately and be referred to a neurologist for further diagnosis and care (see ADVERSE REACTIONS: Neurological).

Serious Skin Reactions

There have been post-marketing reports of erythema multiforme and severe skin reactions [e.g., Stevens-Johnson syndrome (SJS), toxic epidermal necrolysis (TEN)] associated with isotretinoin use. These events may be serious and result in death, life-threatening events, hospitalization, or disability. Patients should be monitored closely for severe skin reactions, and discontinuation of isotretinoin capsules should be considered if warranted.

Pancreatitis

Acute pancreatitishas been reported in patients with either elevated or normal serum triglyceride levels. In rare instances, fatal hemorrhagic pancreatitis has been reported.Isotretinoin capsules should be stopped if hypertriglyceridemia cannot be controlled at an acceptable level or if symptoms of pancreatitis occur.

Lipids

Elevations of serum triglycerides in excess of 800 mg/dL have been reported in patients treated with isotretinoin capsules. Marked elevations of serum triglycerides were reported in approximately 25% of patients receiving isotretinoin capsules in clinical trials. In addition, approximately 15% developed a decrease in high-density lipoproteins and about 7% showed an increase in cholesterol levels. In clinical trials, the effects on triglycerides, HDL, and cholesterol were reversible upon cessation of isotretinoin capsules therapy. Some patients have been able to reverse triglyceride elevation by reduction in weight, restriction of dietary fat and alcohol, and reduction in dose while continuing isotretinoin capsules.^5

Blood lipid determinations should be performed before isotretinoin capsules are given and then at intervals until the lipid response to isotretinoin capsules is established, which usually occurs within 4 weeks. Especially careful consideration must be given to risk/benefit for patients who may be at high risk during isotretinoin capsules therapy (patients with diabetes, obesity, increased alcohol intake, lipid metabolism disorder or familial history of lipid metabolism disorder). If isotretinoin capsules therapy is instituted, more frequent checks of serum values for lipids and/or blood sugar are recommended (see PRECAUTIONS: Laboratory Tests).

The cardiovascular consequences of hypertriglyceridemia associated with isotretinoin capsules are unknown.

Animal Studies

In rats given 8 or 32 mg/kg/day of isotretinoin (1.3 to 5.3 times the recommended clinical dose of 1 mg/kg/day after normalization for total body surface area) for 18 months or longer, the incidences of focal calcification, fibrosis and inflammation of the myocardium, calcification of coronary, pulmonary and mesenteric arteries, and metastatic calcification of the gastric mucosa were greater than in control rats of similar age. Focal endocardial and myocardial calcifications associated with calcification of the coronary arteries were observed in two dogs after approximately 6 to 7 months of treatment with isotretinoin at a dosage of 60 to 120 mg/kg/day (30 to 60 times the recommended clinical dose of 1 mg/kg/day, respectively, after normalization for total body surface area).

Hearing Impairment

Impaired hearing has been reported in patients taking isotretinoin capsules; in some cases, the hearing impairment has been reported to persist after therapy has been discontinued. Mechanism(s) and causality for this event have not been established. Patients who experience tinnitus or hearing impairment should discontinue isotretinoin capsules treatment and be referred for specialized care for further evaluation (see ADVERSE REACTIONS: Special Senses).

Hepatotoxicity

Clinical hepatitis considered to be possibly or probably related to isotretinoin capsules therapy has been reported. Additionally, mild to moderate elevations of liver enzymes have been observed in approximately 15% of individuals treated during clinical trials, some of which normalized with dosage reduction or continued administration of the drug. If normalization does not readily occur or if hepatitis is suspected during treatment with isotretinoin capsules, the drug should be discontinued and the etiology further investigated.

Inflammatory Bowel Disease

Isotretinoin capsules have been associated with inflammatory bowel disease (including regional ileitis) in patients without a prior history of intestinal disorders. In some instances, symptoms have been reported to persist after isotretinoin capsules treatment has been stopped. Patients experiencing abdominal pain, rectal bleeding or severe diarrhea should discontinue isotretinoin capsules immediately (see ADVERSE REACTIONS: Gastrointestinal).

Skeletal

Bone Mineral Density

Effects of multiple courses of isotretinoin capsules on the developing musculoskeletal system are unknown. There is some evidence that long-term, high-dose, or multiple courses of therapy with isotretinoin have more of an effect than a single course of therapy on the musculoskeletal system. In an open-label clinical trial (N=217) of a single course of therapy with isotretinoin capsules for severe recalcitrant nodular acne, bone density measurements at several skeletal sites were not significantly decreased (lumbar spine change >-4% and total hip change >-5%) or were increased in the majority of patients. One patient had a decrease in lumbar spine bone mineral density >4% based on unadjusted data. Sixteen (7.9%) patients had decreases in lumbar spine bone mineral density >4%, and all the other patients (92%) did not have significant decreases or had increases (adjusted for body mass index). Nine patients (4.5%) had a decrease in total hip bone mineral density >5% based on unadjusted data. Twenty-one (10.6%) patients had decreases in total hip bone mineral density >5%, and all the other patients (89%) did not have significant decreases or had increases (adjusted for body mass index). Follow-up studies performed in eight of the patients with decreased bone mineral density for up to 11 months thereafter demonstrated increasing bone density in five patients at the lumbar spine, while the other three patients had lumbar spine bone density measurements below baseline values. Total hip bone mineral densities remained below baseline (range -1.6% to -7.6%) in five of eight patients (62.5%).

In a separate open-label extension study of ten patients, ages 13–18 years, who started a second course of isotretinoin capsules 4 months after the first course, two patients showed a decrease in mean lumbar spine bone mineral density up to 3.25% (see PRECAUTIONS: Pediatric Use).

Spontaneous reports of osteoporosis, osteopenia, bone fractures, and delayed healing of bone fractures have been seen in the isotretinoin capsules population. While causality to isotretinoin capsules have not been established, an effect cannot be ruled out. Longer term effects have not been studied. It is important that isotretinoin capsules be given at the recommended doses for no longer than the recommended duration.

Hyperostosis

A high prevalence of skeletal hyperostosis was noted in clinical trials for disorders of keratinization with a mean dose of 2.24 mg/kg/day. Additionally, skeletal hyperostosis was noted in six of eight patients in a prospective study of disorders of keratinization.^6Minimal skeletal hyperostosis and calcification of ligaments and tendons have also been observed by x–ray in prospective studies of nodular acne patients treated with a single course of therapy at recommended doses. The skeletal effects of multiple isotretinoin capsules treatment courses for acne are unknown.

In a clinical study of 217 pediatric patients (12 to 17 years) with severe recalcitrant nodular acne, hyperostosis was not observed after 16 to 20 weeks of treatment with approximately 1 mg/kg/day of isotretinoin capsules given in two divided doses. Hyperostosis may require a longer time frame to appear. The clinical course and significance remain unknown.

Premature Epiphyseal Closure

There are spontaneous reports of premature epiphyseal closure in acne patients receiving recommended doses of isotretinoin capsules. The effect of multiple courses of isotretinoin capsules on epiphyseal closure is unknown.

Vision Impairment

Visual problems should be carefully monitored. All isotretinoin capsules patients experiencing visual difficulties should discontinue isotretinoin capsules treatment and have an ophthalmological examination (see ADVERSE REACTIONS: Special Senses).

Corneal Opacities

Corneal opacities have occurred in patients receiving isotretinoin capsules for acne and more frequently when higher drug dosages were used in patients with disorders of keratinization. The corneal opacities that have been observed in clinical trial patients treated with isotretinoin capsules have either completely resolved or were resolving at follow-up 6 to 7 weeks after discontinuation of the drug (see ADVERSE REACTIONS: Special Senses).

Decreased night vision has been reported during isotretinoin capsules therapy and in some instances the event has persisted after therapy was discontinued. Because the onset in some patients was sudden, patients should be advised of this potential problem and warned to be cautious when driving or operating any vehicle at night.

PRECAUTIONS

Isotretinoin capsules must only be prescribed by prescribers who are enrolled and activated with the iPLEDGE REMS. Isotretinoin capsules must only be dispensed by a pharmacy enrolled and activated with iPLEDGE, and must only be dispensed to patients who are enrolled andmeet all the requirements of iPLEDGE. Enrolled and activated pharmacies must receive isotretinoin capsules only from wholesalers enrolled with iPLEDGE.

iPLEDGE REMS requirements for wholesalers, prescribers, and pharmacists are described below:

Wholesalers:

For the purpose of the iPLEDGE REMS, the term wholesaler refers to wholesaler, distributor, and/or chain pharmacy distributor. To distribute isotretinoin capsules, wholesalers must be enrolled with iPLEDGE, and agree to meet all iPLEDGE requirements for wholesale distribution of isotretinoin products. Wholesalers must enroll with iPLEDGE by signing and returning the iPLEDGE wholesaler agreement that affirms they will comply with all iPLEDGE requirements for distribution of isotretinoin. These include:

- Enrolling prior to distributing isotretinoin and re-enrolling annually thereafter
- Distributing only FDA approved isotretinoin product
- Only shipping isotretinoin to
  1. wholesalers enrolled in the iPLEDGE REMS with prior written consent from the manufacturer or
  2. pharmacies licensed in the US and enrolled and activated in the iPLEDGE REMS
- Notifying the isotretinoin manufacturer (or delegate) of any non-enrolled and/or non-activated pharmacy or unenrolled wholesaler that attempts to order isotretinoin
- Complying with inspection of wholesaler records for verification of compliance with the iPLEDGE REMS by the isotretinoin manufacturer (or delegate)
- Returning to the manufacturer (or delegate) any undistributed product if the wholesaler is deactivated by the iPLEDGE REMS or if the wholesaler chooses to not re-enroll annually

Prescribers

To prescribe isotretinoin, the prescriber must be enrolled and activated with the pregnancy risk management program iPLEDGE. Prescribers can enroll by signing and returning the completed enrollment form. Prescribers can only activate their enrollment by affirming that they meet requirements and will comply with all iPLEDGE requirements by attesting to the following points:

- I know the risk and severity of fetal injury/birth defects from isotretinoin.
- I know the risk factors for unplanned pregnancy and the effective measures for avoidance of unplanned pregnancy.
- I have the expertise to provide the patient with detailed pregnancy prevention counseling, or I will refer the patient to an expert for such counseling, reimbursed by the manufacturer.
- I will comply with the iPLEDGE REMS requirements described in the booklet entitled iPLEDGE REMS Prescriber Guide.
- Before beginning treatment of patients who can become pregnant with isotretinoin, and on a monthly basis, the patient will be counseled to avoid pregnancy by using two forms of contraception simultaneously and continuously for at least one month prior to initiation of isotretinoin treatment, during isotretinoin treatment and for one month after discontinuing isotretinoin treatment, unless the patient commits to continuous abstinence, not having any sexual contact with a partner that could result in pregnancy.
- I will not prescribe isotretinoin to any patient who can become pregnant until verifying the patient has a negative screening pregnancy test and monthly negative CLIA-certified (Clinical Laboratory Improvement Amendment) pregnancy tests. Patients should have a pregnancy test at the completion of the entire course of isotretinoin and another pregnancy test one month later.
- I will report any pregnancy case that I become aware of while the patient who can become pregnant is on isotretinoin or one month after the last dose to the pregnancy registry.

To prescribe isotretinoin, the prescriber must access the iPLEDGE system via the internet (www.ipledgeprogram.com) or telephone (1-866-495-0654) to:

1. Register each patient in the iPLEDGE REMS.
2. Confirm monthly that each patient has received counseling and education .
3. For patients who can become pregnant:
  - Enter patient's two chosen forms of contraception each month.
  - Enter monthly result from CLIA-certified laboratory conducted pregnancy test.

Isotretinoin must only be prescribed to patients who are known not to be pregnant as confirmed by a negative CLIA-certified laboratory conducted pregnancy test.

Isotretinoin must only be dispensed by a pharmacy enrolled and activated with the pregnancy risk management program iPLEDGE and only when the enrolled patient meets all the requirements of the iPLEDGE REMS. Meeting the requirements for a patient who can become pregnant signifies that the patient:

- Hasbeen counseled and has signed a Patient Enrollment Form for Patients who can get Pregnant that contains warnings about the risk of potential birth defects if the fetus is exposed to isotretinoin. The patient must sign the informed consent form before starting treatment and patient counseling must also be done at that time and on a monthly basis thereafter.
- Hashad two negative urine or serum pregnancy tests with a sensitivity of at least 25 mIU/mL before receiving the initial isotretinoin prescription. The first test (a screening test) is obtained by the prescriber when the decision is made to pursue qualification of the patient for isotretinoin. The second pregnancy test (a confirmation test) must be done in a CLIA-certified laboratory. The interval between the two tests should be at least 19 days.
  1. For patients with regular menstrual cycles, the second pregnancy test should be done during the first 5 days of the menstrual period immediately preceding the beginning of isotretinoin therapy and after the patient has used two forms of contraception for one month.
  2. For patients with amenorrhea, irregular cycles, or using a contraceptive form that precludes withdrawal bleeding, the second pregnancy test must be done immediately preceding the beginning of isotretinoin therapy and after the patient has used two forms of contraception for one month.
- Has hada negative result from a urine or serum pregnancy test in a CLIA-certified laboratory before receiving each subsequent course of isotretinoin. A pregnancy test must be repeated every month, in a CLIA-certified laboratory, prior to the patient who can become pregnant receiving each prescription.
- Hasselected and has committed to use two forms of effective contraception simultaneously, at least one of which must be a primary form, unless the patient commits to continuous abstinence not having any sexual contact with a partner that could result in pregnancy, or the patient has undergone a hysterectomy or bilateral oophorectomy, or has been medically confirmed to be post-menopausal. Patients must use two forms of effective contraception for at least one month prior to initiation of isotretinoin therapy, during isotretinoin therapy, and for one month after discontinuing isotretinoin therapy. Counseling about contraception and behaviors associated with an increased risk of pregnancy must be repeated on a monthly basis.

If the patient has unprotected sexual contact with a partner that could result in pregnancy at any time one month before, during, or one month after therapy, the patient must:

1. Stop taking isotretinoin capsules immediately, if on therapy
2. Have a pregnancy test at least 19 days after the last act of unprotected sexual contact with a partner that could result in pregnancy
3. Start using two forms of effective contraception simultaneously again for one month before resuming isotretinoin capsules therapy
4. Have a second pregnancy test after using two forms of effective contraception for one month as described above depending on whether the patient has regular menses or not.

Effective forms of contraception include both primary and secondary forms of contraception:

Primary forms | Secondary forms
- tubal sterilization - male vasectomy - intrauterine device - hormonal (combination oral contraceptives, transdermal patch, injectables, implantables, or vaginal ring) | Barrier:; - male latex condom with or without spermicide - diaphragm with spermicide - cervical cap with spermicide; Other:; - vaginal sponge (contains spermicide)

Any birth control method can fail. There have been reports of pregnancy from patients who can become pregnant who have used oral contraceptives, as well as transdermal patch/injectable/implantable/vaginal ring hormonal birth control products; these pregnancies occurred while these patients were taking isotretinoin capsules. These reports are more frequent for patients who use only a single form of contraception. Therefore, it is critically important that patients who can become pregnant use two effective forms of contraception simultaneously. Patients must receive warnings about the rates of possible contraception failure importance of choosing one primary form and a secondary form of contraception and that the patient must be compliant in use as outlined in the Guide for Patients who can get Pregnant.

Using two forms of contraception simultaneously substantially reduces the chances that a patient will become pregnant over the risk of pregnancy with either form alone. A drug interaction that decreases effectiveness of hormonal contraceptives has not been entirely ruled out for isotretinoin capsules (see PRECAUTIONS: Drug Interactions). Although hormonal contraceptives are highly effective, prescribers are advised to consult the package insert of any medication administered concomitantly with hormonal contraceptives, since some medications may decrease the effectiveness of these birth control products. Patients should be prospectively cautioned not to self-medicate with the herbal supplement St. John's Wort because a possible interaction has been suggested with hormonal contraceptives based on reports of breakthrough bleeding on oral contraceptives shortly after starting St. John's Wort. Pregnancies have been reported by users of combined hormonal contraceptives who also used some form of St. John's Wort.

If a pregnancy does occur during isotretinoin capsules treatment, isotretinoin capsules must be discontinued immediately. The patient should be referred to an Obstetrician-Gynecologist experienced in reproductive toxicity for further evaluation and counseling. Any suspected fetal exposure during or one month after isotretinoin capsules therapy must be reported immediately to the FDA via the MedWatch number 1-800-FDA-1088 and also to the iPLEDGE Pregnancy Registry at 1-866-495-0654 or via the internet (www.ipledgeprogram.com).

All Patients

Isotretinoin is contraindicated in patients who are pregnant. To receive isotretinoin all patients must meet all of the following conditions:

- Mustbe enrolled with the iPLEDGE REMS by the prescriber
- Mustunderstand that life-threatening birth defects can occur with the use of isotretinoin by patients who can become pregnant
- Mustbe reliable in understanding and carrying out instructions
- Mustsign a Patient Enrollment Form for Patients who cannot get Pregnant that contains warnings about the potential risks associated with isotretinoin
- Mustobtain the prescription within 7 days of the date of specimen collection for the pregnancy test for patients who can become pregnant
- Mustobtain the prescription within 30 days of the office visit for patients who cannot become pregnant
- Mustnot donate blood while on isotretinoin and for one month after treatment has ended
- Mustnot share isotretinoin with anyone, even someone who has similar symptoms

Patients Who Can Become Pregnant

Isotretinoin is contraindicated in patients who are pregnant. In addition to the requirements for all patients described above, patients who can become pregnant must meet the following conditions:

- MustNOT be pregnant or breast-feeding
- Mustcomply with the required pregnancy testing at a CLIA-certified laboratory
- Mustobtain the prescription within 7 days of the date of specimen collection for the pregnancy test
- Mustbe capable of complying with the mandatory contraceptive measures required for isotretinoin therapy, or commit to continuous abstinence not having any sexual contact with a partner that could result in pregnancy, and understand behaviors associated with an increased risk of pregnancy
- Mustunderstand that it is the patient who can become pregnant responsibility to avoid pregnancy one month before, during and one month after isotretinoin therapy
- Musthave signed an additional Patient Enrollment Form for Patients who can get Pregnant, before starting isotretinoin, that contains warnings about the risk of potential birth defects if the fetus is exposed to isotretinoin
- Mustaccess the iPLEDGE system via the internet (www.ipledgeprogram.com) or telephone (1-866-495-0654), before starting isotretinoin, on a monthly basis during therapy, and one month after the last dose to answer questions on the program requirements and to enter the patient's two chosen forms of contraception
- Musthave been informed of the purpose and importance of providing information to the iPLEDGE REMS should the patient become pregnant while taking isotretinoin or within one month of the last dose

Pharmacists

To dispense isotretinoin, pharmacies must be enrolled and activated with the pregnancy risk management program iPLEDGE.

The Responsible Site Pharmacist must enroll the pharmacy by signing and returning the completed Pharmacy Enrollment Form. After enrolling, the Responsible Site Pharmacist can only activate the pharmacy enrollment by affirming that they meet requirements and will comply with all iPLEDGE requirements by attesting to the following points:

- I know the risk and severity of fetal injury/birth defects from isotretinoin.
- I will train all pharmacists who participate in the filling and dispensing of isotretinoin prescriptions on the iPLEDGE REMS requirements.
- I will comply and seek to ensure all pharmacists who participate in the filling and dispensing of isotretinoin prescriptions comply with the iPLEDGE REMS requirements described in the booklet entitled Pharmacist Guide,specifically the "Key Information for Pharmacists" section including the following dispensing information:
  1. Prescriptions must be obtained no later than the "Do Not Dispense To After" date, and if not obtained, then the RMA must be reversed in the iPLEDGE REMS system and the product returned to inventory.
- I understand and will comply with Non-Compliance Action Policy.
- I will only obtain isotretinoin capsules product from only iPLEDGE enrolled wholesalers.
- I will not sell, buy, borrow, loan or otherwise transfer isotretinoin in any manner to or from another pharmacy.
- I will return to the manufacturer (or delegate) any unused product if the pharmacy is deactivated by the iPLEDGE REMS or if the pharmacy chooses to not reactivate annually.
- I will not fill isotretinoin for any party other than a qualified patient.
- I will comply with the audits by the iPLEDGE Sponsors or third party acting on behalf of the iPLEDGE Sponsors to ensure that all processes and procedures are in place and being followed for the iPLEDGE REMS

To dispense isotretinoin, the pharmacist must:

1. be trained by the Responsible Site Pharmacist concerning the iPLEDGE REMS requirements.
2. obtain authorization from the iPLEDGE REMS via the internet (www.ipledgeprogram.com), or telephone (1-866-495-0654) for every isotretinoin prescription. Authorization signifies that the patient has met all program requirements and is qualified to receive isotretinoin capsules.
3. write the Risk Management Authorization (RMA) number on the prescription.

Isotretinoin capsules must only be dispensed:

- in no more than a 30-day supply
- with an isotretinoin capsules Medication Guide
- after authorization from the iPLEDGE REMS
- prior to the "do not dispense to patient after" date provided by the iPLEDGE system (within 30 days of the office visit for patients who cannot become pregnant and within 7 days of the date of specimen collection for patients who can become pregnant)
- with a new prescription for refills and another authorization from the iPLEDGE REMS (No automatic refills are allowed)

An isotretinoin capsules Medication Guide must be given to the patient each time isotretinoin capsules is dispensed, as required by law. This isotretinoin capsules Medication Guide is an important part of the risk management program for the patients.

Isotretinoin capsules must not be prescribed, dispensed or otherwise obtained through the internet or any other means outside of the iPLEDGE REMS. Only FDA-approved isotretinoin capsules products must be distributed, prescribed, dispensed, and used. Patients must obtain isotretinoin capsules prescriptions only at US licensed pharmacies.

A description of the iPLEDGE REMS educational materials available with iPLEDGE is provided below. The main goal of these educational materials is to explain the iPLEDGE REMS requirements and to reinforce the educational messages.

1. Prescriber Guideincludes: isotretinoin teratogenic potential, information on pregnancy testing, and the method to complete a qualified isotretinoin capsules prescription.
2. Pharmacist Guideincludes: isotretinoin teratogenic potential and the method to obtain authorization to dispense an isotretinoin prescription.
3. The iPLEDGE REMS is a systematic approach to comprehensive patient education about their responsibilities and includes education for contraception compliance and reinforcement of educational messages. The iPLEDGE REMS includes information on the risks and benefits of isotretinoin capsules which is linked to the Medication Guide dispensed by pharmacists with each isotretinoin prescription.
4. The Fact Sheet for the iPLEDGE REMS includes information on the iPLEDGE REMS, the product indications and safety information. This handout is provided to both the patient who can become pregnant and the patient who cannot become pregnant. The Patient Enrollment Form for Patients who cannot get Pregnant is also provided to all patients.
5. Patients who can become pregnant are provided with a Guide for Patients who Can Get Pregnant, which contains information on isotretinoin therapy including precautions and warnings, and a second Patient Enrollment Form for Patients who can get Pregnant concerning birth defects, and a toll-free line which provides isotretinoin capsules information in two languages.
6. The booklet for patients who can become pregnant, Contraception Counseling Guide, includes a referral program that offers patients free contraception counseling, reimbursed by the manufacturer, by a reproductive specialist and a second Patient Enrollment Form for Patients who can get Pregnant concerning birth defects.
7. The Guide for Patients Who Can Get Pregnantoutlines the effectiveness of the approved contraception options. (see Information for Patients).

General

Although an effect of isotretinoin capsules on bone loss is not established, physicians should use caution when prescribing isotretinoin capsules to patients with a genetic predisposition for age-related osteoporosis, a history of childhood osteoporosis conditions, osteomalacia, or other disorders of bone metabolism. This would include patients diagnosed with anorexia nervosa and those who are on chronic drug therapy that causes drug-induced osteoporosis/osteomalacia and/or affects vitamin D metabolism, such as systemic corticosteroids and any anticonvulsant.

Patients may be at increased risk when participating in sports with repetitive impact where the risks of spondylolisthesis with and without pars fractures and hip growth plate injuries in early and late adolescence are known. There are spontaneous reports of fractures and/or delayed healing in patients while on therapy with isotretinoin capsules or following cessation of therapy with isotretinoin capsules while involved in these activities. While causality to isotretinoin capsules has not been established, an effect must not be ruled out.

Information for Patients

See PRECAUTIONSand Boxed CONTRAINDICATIONS AND WARNINGS.

- Patients must be instructed to read the Medication Guide supplied as required by law when isotretinoin capsules are dispensed. The complete text of the Medication Guide is reprinted at the end of this document. For additional information, patients must also be instructed to read the iPLEDGE REMS patient educational materials. All patients must sign the Patient Enrollment Form for Patients who cannot get Pregnant.
- Patients who can become pregnant must be instructed that they must not be pregnant when isotretinoin capsules therapy is initiated, and that they should use two forms of effective contraception simultaneously for one month before starting isotretinoin capsules, while taking isotretinoin capsules and for one month after isotretinoin capsules have been stopped, unless they commit to continuous abstinence from not having any sexual contact with a partner that could result in pregnancy. They should also sign a second Patient Enrollment Form for Patients who can get Pregnant prior to beginning isotretinoin capsules therapy. Patients who can become pregnant should be seen by their prescribers monthly and have a urine or serum pregnancy test, in a CLIA-certified laboratory, performed each month during treatment to confirm negative pregnancy status before another isotretinoin capsules prescription is written (see Boxed CONTRAINDICATIONS AND WARNINGSand PRECAUTIONS).
- Isotretinoin is found in the semen of male patients taking isotretinoin capsules, but the amount delivered to a patient who can become pregnant would be about one million times lower than an oral dose of 40 mg. While the no-effect limit for isotretinoin induced embryopathy is unknown, 20 years of postmarketing reports include four with isolated defects compatible with features of retinoid exposed fetuses; however two of these reports were incomplete, and two had other possible explanations for the defects observed.
- Prescribers should be alert to the warning signs of psychiatric disorders to guide patients to receive the help they need. Therefore, prior to initiation of isotretinoin capsules treatment, patients and family members should be asked about any history of psychiatric disorder, and at each visit during treatment patients should be assessed for symptoms of depression, mood disturbance, psychosis, or aggression to determine if further evaluation may be necessary. Signs and symptoms of depression include sad mood, hopelessness, feelings of guilt, worthlessness or helplessness, loss of pleasure or interest in activities, fatigue, difficulty concentrating, change in sleep pattern, change in weight or appetite, suicidal thoughts or attempts, restlessness, irritability, acting on dangerous impulses, and persistent physical symptoms unresponsive to treatment.Patients should stop isotretinoin capsules and the patient or a family member should promptly contact their prescriber if the patient develops depression, mood disturbance, psychosis, or aggression, without waiting until the next visit. Discontinuation of isotretinoin capsules treatment may be insufficient; further evaluation may be necessary. While such monitoring may be helpful, it may not detect all patients at risk. Patients may report mental health problems or family history of psychiatric disorders. These reports should be discussed with the patient and/or the patient's family. A referral to a mental health professional may be necessary. The physician should consider whether isotretinoin capsules therapy is appropriate in this setting; for some patients the risks may outweigh the benefits of isotretinoin capsules therapy.
- Patients must be informed that some patients, while taking isotretinoin capsules or soon after stopping isotretinoin capsules, have become depressed or developed other serious mental problems. Symptoms of depression include sad, "anxious" or empty mood, irritability, acting on dangerous impulses, anger, loss of pleasure or interest in social or sports activities, sleeping too much or too little, changes in weight or appetite, school or work performance going down, or trouble concentrating. Some patients taking isotretinoin capsules have had thoughts about hurting themselves or putting an end to their own lives (suicidal thoughts). Some people tried to end their own lives. And some people have ended their own lives. There were reports that some of these people did not appear depressed. There have been reports of patients on isotretinoin capsules becoming aggressive or violent. No one knows if isotretinoin caused these behaviors or if they would have happened even if the person did not take isotretinoin capsules. Some people have had other signs of depression while taking isotretinoin capsules.
- Patients must be informed that they must not share isotretinoin capsules with anyone else because of the risk of birth defects and other serious adverse events.
- Patients must be informed not to donate blood during therapy and for one month following discontinuation of the drug because the blood might be given to a pregnant patient whose fetus must not be exposed to isotretinoin capsules.
- Patients should be reminded to take isotretinoin capsules with a meal (see DOSAGE AND ADMINISTRATION). To decrease the risk of esophageal irritation, patients should swallow the capsules with a full glass of liquid.
- Patients should be informed that transient exacerbation (flare) of acne has been seen, generally during the initial period of therapy.
- Wax epilation and skin resurfacing procedures (such as dermabrasion, laser) should be avoided during isotretinoin capsules therapy and for at least 6 months thereafter due to the possibility of scarring (see ADVERSE REACTIONS: Skin and Appendages).
- Patients should be advised to avoid prolonged exposure to UV rays or sunlight.
- Patients should be informed that they may experience decreased tolerance to contact lenses during and after therapy.
- Patients should be informed that approximately 16% of patients treated with isotretinoin capsules in a clinical trial developed musculoskeletal symptoms (including arthralgia) during treatment. In general, these symptoms were mild to moderate, but occasionally required discontinuation of the drug. Transient pain in the chest has been reported less frequently. In the clinical trial, these symptoms generally cleared rapidly after discontinuation of isotretinoin capsules, but in some cases persisted (see ADVERSE REACTIONS: Musculoskeletal). There have been rare postmarketing reports of rhabdomyolysis, some associated with strenuous physical activity (see Laboratory Tests: CPK).
- Pediatric patients and their caregivers should be informed that approximately 29% (104/358) of pediatric patients treated with isotretinoin capsules developed back pain. Back pain was severe in 13.5% (14/104) of the cases and occurred at a higher frequency in female patients than male patients. Arthralgias were experienced in 22% (79/358) of pediatric patients. Arthralgias were severe in 7.6% (6/79) of patients. Appropriate evaluation of the musculoskeletal system should be done in patients who present with these symptoms during or after a course of isotretinoin capsules. Consideration should be given to discontinuation of isotretinoin capsules if any significant abnormality is found.
- Neutropenia and rare cases of agranulocytosis have been reported. Isotretinoin capsules should be discontinued if clinically significant decreases in white cell counts occur.
- Patients should be advised that severe skin reactions (Stevens-Johnson syndrome and toxic epidermal necrolysis) have been reported in post-marketing data. Isotretinoin capsules should be discontinued if clinically significant skin reactions occur.

Hypersensitivity

Anaphylactic reactions and other allergic reactions have been reported. Cutaneous allergic reactions and serious cases of allergic vasculitis, often with purpura (bruises and red patches) of the extremities and extracutaneous involvement (including renal) have been reported. Severe allergic reaction necessitates discontinuation of therapy and appropriate medical management.

Drug Interactions

- Vitamin A:Because of the relationship of isotretinoin capsules to vitamin A, patients should be advised against taking vitamin supplements containing vitamin A to avoid additive toxic effects.
- Tetracyclines:Concomitant treatment with isotretinoin capsules and tetracyclines should be avoided because isotretinoin capsules use has been associated with a number of cases of pseudotumor cerebri (benign intracranial hypertension), some of which involved concomitant use of tetracyclines.
- Micro-dosed Progesterone Preparations:Micro-dosed progesterone preparations ("minipills" that do not contain an estrogen) may be an inadequate method of contraception during isotretinoin capsules therapy. Although other hormonal contraceptives are highly effective, there have been reports of pregnancy from patients who can become pregnant who have used combined oral contraceptives, as well as transdermal patch/injectable/implantable/vaginal ring hormonal birth control products. These reports are more frequent for patients who can become pregnant who use only a single form of contraception. It is not known if hormonal contraceptives differ in their effectiveness when used with isotretinoin capsules. Therefore, it is critically important for patients who can become pregnant to select and commit to use two forms of effective contraception simultaneously, at least one of which must be a primary form (see PRECAUTIONS).
- Norethindrone/ethinyl estradiol:In a study of 31 premenopausal female patients with severe recalcitrant nodular acne receiving OrthoNovum®7/7/7 Tablets as an oral contraceptive agent, isotretinoin capsules at the recommended dose of 1 mg/kg/day, did not induce clinically relevant changes in the pharmacokinetics of ethinyl estradiol and norethindrone and in the serum levels of progesterone, follicle-stimulating hormone (FSH) and luteinizing hormone (LH). Prescribers are advised to consult the package insert of medication administered concomitantly with hormonal contraceptives, since some medications may decrease the effectiveness of these birth control products.
- St. John's Wort: Isotretinoin capsules use is associated with depression in some patients(see WARNINGS: Psychiatric Disordersand ADVERSE REACTIONS: Psychiatric). Patients should be prospectively cautioned not to self-medicate with the herbal supplement St. John's Wort because a possible interaction has been suggested with hormonal contraceptives based on reports of breakthrough bleeding on oral contraceptives shortly after starting St. John's Wort. Pregnancies have been reported by users of combined hormonal contraceptives who also used some form of St. John's Wort.
- Phenytoin: Isotretinoin capsules have not been shown to alter the pharmacokinetics of phenytoin in a study in seven healthy volunteers. These results are consistent with the in vitro finding that neither isotretinoin nor its metabolites induce or inhibit the activity of the CYP 2C9 human hepatic P450 enzyme. Phenytoin is known to cause osteomalacia. No formal clinical studies have been conducted to assess if there is an interactive effect on bone loss between phenytoin and isotretinoin capsules. Therefore, caution should be exercised when using these drugs together.
- Systemic Corticosteroids:Systemic corticosteroids are known to cause osteoporosis. No formal clinical studies have been conducted to assess if there is an interactive effect on bone loss between systemic corticosteroids and isotretinoin capsules. Therefore, caution should be exercised when using these drugs together.

Laboratory Tests

- Pregnancy Test:
  1. Patients who can become pregnant musthave had two negative urine or serum pregnancy tests with a sensitivity of at least 25 mIU/mL before receiving the initial isotretinoin capsules prescription. The first test (a screening test) is obtained by the prescriber when the decision is made to pursue qualification of the patient for isotretinoin capsules. The second pregnancy test (a confirmation test) must be done in a CLIA-certified laboratory. The interval between the two tests must be at least 19 days.
  2. For patients with regular menstrual cycles, the second pregnancy test must be done during the first 5 days of the menstrual period immediately preceding the beginning of isotretinoin therapy and after the patient has used 2 forms of contraception for 1 month.
  3. For patients with amenorrhea, irregular cycles, or using a contraceptive method that precludes withdrawal bleeding, the second pregnancy test must be done immediately preceding the beginning of isotretinoin therapy and after the patient has used 2 forms of contraception for 1 month.
  4. Each month of therapy, patients must have a negative result from a urine or serum pregnancy test. A pregnancy test must be repeated each month, in a CLIA-certified laboratory, prior to the patient who can become pregnant receiving each prescription.
- Lipids:Pretreatment and follow-up blood lipids should be obtained under fasting conditions. After consumption of alcohol, at least 36 hours should elapse before these determinations are made. It is recommended that these tests be performed at weekly or biweekly intervals until the lipid response to isotretinoin is established. The incidence of hypertriglyceridemia is one patient in four on isotretinoin therapy (see WARNINGS: Lipids).
- Liver Function Tests:Since elevations of liver enzymes have been observed during clinical trials, and hepatitis has been reported, pretreatment and follow-up liver function tests should be performed at weekly or biweekly intervals until the response to isotretinoin has been established (see WARNINGS: Hepatotoxicity).
- Glucose:Some patients receiving isotretinoin have experienced problems in the control of their blood sugar. In addition, new cases of diabetes have been diagnosed during isotretinoin therapy, although no causal relationship has been established.
- CPK:Some patients undergoing vigorous physical activity while on isotretinoin therapy have experienced elevated CPK levels; however, the clinical significance is unknown. There have been rare postmarketing reports of rhabdomyolysis, some associated with strenuous physical activity. In a clinical trial of 217 pediatric patients (12 to 17 years) with severe recalcitrant nodular acne, transient elevations in CPK were observed in 12% of patients, including those undergoing strenuous physical activity in association with reported musculoskeletal adverse events such as back pain, arthralgia, limb injury, or muscle sprain. In these patients, approximately half of the CPK elevations returned to normal within 2 weeks and half returned to normal within 4 weeks. No cases of rhabdomyolysis were reported in this trial.

Carcinogenesis, Mutagenesis and Impairment of Fertility

In male and female Fischer 344 rats given oral isotretinoin at dosages of 8 or 32 mg/kg/day (1.3 to 5.3 times the recommended clinical dose of 1 mg/kg/day, respectively, after normalization for total body surface area) for greater than 18 months, there was a dose-related increased incidence of pheochromocytoma relative to controls. The incidence of adrenal medullary hyperplasia was also increased at the higher dosage in both sexes. The relatively high level of spontaneous pheochromocytomas occurring in the male Fischer 344 rat makes it an equivocal model for study of this tumor; therefore, the relevance of this tumor to the human population is uncertain.

The Ames test was conducted with isotretinoin in two laboratories. The results of the tests in one laboratory were negative while in the second laboratory a weakly positive response (less than 1.6× background) was noted in S. typhimuriumTA100 when the assay was conducted with metabolic activation. No dose response effect was seen and all other strains were negative. Additionally, other tests designed to assess genotoxicity (Chinese hamster cell assay, mouse micronucleus test, S. cerevisiaeD7 assay, in vitro clastogenesis assay with human-derived lymphocytes, and unscheduled DNA synthesis assay) were all negative.

In rats, no adverse effects on gonadal function, fertility, conception rate, gestation or parturition were observed at oral dosages of isotretinoin of 2, 8, or 32 mg/kg/day (0.3, 1.3, or 5.3 times the recommended clinical dose of 1 mg/kg/day, respectively, after normalization for total body surface area).

In dogs, testicular atrophy was noted after treatment with oral isotretinoin for approximately 30 weeks at dosages of 20 or 60 mg/kg/day (10 or 30 times the recommended clinical dose of 1 mg/kg/day, respectively, after normalization for total body surface area). In general, there was microscopic evidence for appreciable depression of spermatogenesis but some sperm were observed in all testes examined and in no instance were completely atrophic tubules seen. In studies of 66 men, 30 of whom were patients with nodular acne under treatment with oral isotretinoin, no significant changes were noted in the count or motility of spermatozoa in the ejaculate. In a study of 50 men (ages 17 to 32 years) receiving isotretinoin therapy for nodular acne, no significant effects were seen on ejaculate volume, sperm count, total sperm motility, morphology or seminal plasma fructose.

Pregnancy

Category X

See Boxed CONTRAINDICATIONS AND WARNINGS.

Nursing Mothers

It is not known whether this drug is excreted in human milk. Because of the potential for adverse effects, nursing mothers should not receive isotretinoin capsules.

Pediatric Use

The use of isotretinoin capsules in pediatric patients less than 12 years of age has not been studied. The use of isotretinoin capsules for the treatment of severe recalcitrant nodular acne in pediatric patients ages 12 to 17 years should be given careful consideration, especially for those patients where a known metabolic or structural bone disease exists (see PRECAUTIONS: General). Use of isotretinoin capsules in this age group for severe recalcitrant nodular acne is supported by evidence from a clinical study comparing 103 pediatric patients (13 to 17 years) to 197 adult patients (≥18 years). Results from this study demonstrated that isotretinoin, at a dose of 1 mg/kg/day given in two divided doses, was equally effective in treating severe recalcitrant nodular acne in both pediatric and adult patients. In studies with isotretinoin, adverse reactions reported in pediatric patients were similar to those described in adults except for the increased incidence of back pain and arthralgia (both of which were sometimes severe) and myalgia in pediatric patients (see ADVERSE REACTIONS).

In an open-label clinical trial (N=217) of a single course of therapy with isotretinoin for severe recalcitrant nodular acne, bone density measurements at several skeletal sites were not significantly decreased (lumbar spine change >-4% and total hip change >-5%) or were increased in the majority of patients. One patient had a decrease in lumbar spine bone mineral density >4% based on unadjusted data. Sixteen (7.9%) patients had decreases in lumbar spine bone mineral density >4%, and all the other patients (92%) did not have significant decreases or had increases (adjusted for body mass index). Nine patients (4.5%) had a decrease in total hip bone mineral density >5% based on unadjusted data. Twenty-one (10.6%) patients had decreases in total hip bone mineral density >5%, and all the other patients (89%) did not have significant decreases or had increases (adjusted for body mass index). Follow-up studies performed in eight of the patients with decreased bone mineral density for up to 11 months thereafter demonstrated increasing bone density in five patients at the lumbar spine, while the other three patients had lumbar spine bone density measurements below baseline values. Total hip bone mineral densities remained below baseline (range -1.6% to -7.6%) in five of eight patients (62.5%).

In a separate open-label extension study of ten patients, ages 13 to 18 years, who started a second course of isotretinoin 4 months after the first course, two patients showed a decrease in mean lumbar spine bone mineral density up to 3.25% (see WARNINGS: Skeletal: Bone Mineral Density).

Geriatric Use

Clinical studies of isotretinoin did not include sufficient numbers of subjects aged 65 years and over to determine whether they respond differently from younger subjects. Although reported clinical experience has not identified differences in responses between elderly and younger patients, effects of aging might be expected to increase some risks associated with isotretinoin therapy (see WARNINGSand PRECAUTIONS).

ADVERSE REACTIONS

Clinical Trials and Postmarketing Surveillance

The adverse reactions listed below reflect the experience from investigational studies of isotretinoin , and the postmarketing experience. The relationship of some of these events to isotretinoin therapy is unknown. Many of the side effects and adverse reactions seen in patients receiving isotretinoin are similar to those described in patients taking very high doses of vitamin A (dryness of the skin and mucous membranes, e.g. of the lips, nasal passage, and eyes).

Dose Relationship

Cheilitis and hypertriglyceridemia are usually dose related. Most adverse reactions reported in clinical trials were reversible when therapy was discontinued; however, some persisted after cessation of therapy (see WARNINGSand ADVERSE REACTIONS).

Body as a Whole

allergic reactions, including vasculitis, systemic hypersensitivity (see PRECAUTIONS: Hypersensitivity), edema, fatigue, lymphadenopathy, weight loss

Cardiovascular

palpitation, tachycardia, vascular thrombotic disease, stroke

Endocrine/Metabolic

hypertriglyceridemia (see WARNINGS: Lipids), alterations in blood sugar levels (see PRECAUTIONS: Laboratory Tests).

Gastrointestinal

inflammatory bowel disease (see WARNINGS: Inflammatory Bowel Disease), hepatitis (see WARNINGS: Hepatotoxicity), pancreatitis (see WARNINGS: Lipids), bleeding and inflammation of the gums, colitis, esophagitis/esophageal ulceration, ileitis, nausea, other nonspecific gastrointestinal symptoms.

Hematologic

allergic reactions (see PRECAUTIONS: Hypersensitivity), anemia, thrombocytopenia, neutropenia, rare reports of agranulocytosis (see PRECAUTIONS: Information for Patients). See PRECAUTIONS: Laboratory Testsfor other hematological parameters.

Musculoskeletal

skeletal hyperostosis, calcification of tendons and ligaments, premature epiphyseal closure, decreases in bone mineral density (see WARNINGS: Skeletal), musculoskeletal symptoms (sometimes severe) including back pain, myalgia, and arthralgia (see PRECAUTIONS: Information for Patients), transient pain in the chest (see PRECAUTIONS: Information for Patients), arthritis, tendonitis, other types of bone abnormalities, elevations of CPK/rare reports of rhabdomyolysis (see PRECAUTIONS: Laboratory Tests).

Neurological

pseudotumor cerebri (see WARNINGS: Pseudotumor Cerebri), dizziness, drowsiness, headache, insomnia, lethargy, malaise, nervousness, paresthesias, seizures, stroke, syncope, weakness.

Psychiatric

suicidal ideation, suicide attempts, suicide, depression, psychosis, aggression, violent behaviors (see WARNINGS: Psychiatric Disorders), emotional instability.

Of the patients reporting depression, some reported that the depression subsided with discontinuation of therapy and recurred with reinstitution of therapy.

Reproductive System

Abnormal menses.

Respiratory

bronchospasms (with or without a history of asthma), respiratory infection, voice alteration

Skin and Appendages

acne fulminans, alopecia (which in some cases persists), bruising, cheilitis (dry lips), dry mouth, dry nose, dry skin, epistaxis, eruptive xanthomas,^7erythema multiforme, flushing, fragility of skin, hair abnormalities, hirsutism, hyperpigmentation and hypopigmentation, infections (including disseminated herpes simplex), nail dystrophy, paronychia, peeling of palms and soles, photoallergic/photosensitizing reactions, pruritus, pyogenic granuloma, rash (including facial erythema, seborrhea, and eczema), Stevens-Johnson syndrome, sunburn susceptibility increased, sweating, toxic epidermal necrolysis, urticaria, vasculitis (including Wegener's granulomatosis; see PRECAUTIONS: Hypersensitivity), abnormal wound healing (delayed healing or exuberant granulation tissue with crusting; see PRECAUTIONS: Information for Patients)

Special Senses

Hearing

hearing impairment (see WARNINGS: Hearing Impairment), tinnitus.

Vision

corneal opacities (see WARNINGS: Corneal Opacities), decreased night vision which may persist (see WARNINGS: Decreased Night Vision), cataracts, color vision disorder, conjunctivitis, dry eyes, eyelid inflammation, keratitis, optic neuritis, photophobia, visual disturbances

Urinary System

glomerulonephritis (see PRECAUTIONS: Hypersensitivity), nonspecific urogenital findings (see PRECAUTIONS: Laboratory Testsfor other urological parameters)

Laboratory

Elevation of plasma triglycerides (see WARNINGS: Lipids), decrease in serum high-density lipoprotein (HDL) levels, elevations of serum cholesterol during treatment

Increased alkaline phosphatase, SGOT (AST), SGPT (ALT), GGTP or LDH (see WARNINGS: Hepatotoxicity)

Elevation of fasting blood sugar, elevations of CPK (see PRECAUTIONS: Laboratory Tests), hyperuricemia

Decreases in red blood cell parameters, decreases in white blood cell counts (including severe neutropenia and rare reports of agranulocytosis; see PRECAUTIONS: Information for Patients), elevated sedimentation rates, elevated platelet counts, thrombocytopenia

White cells in the urine, proteinuria, microscopic or gross hematuria

OVERDOSAGE

The oral LD50of isotretinoin is greater than 4000 mg/kg in rats and mice (>600 times the recommended clinical dose of 1 mg/kg/day after normalization of the rat dose for total body surface area and >300 times the recommended clinical dose of 1 mg/kg/day after normalization of the mouse dose for total body surface area) and is approximately 1960 mg/kg in rabbits (653 times the recommended clinical dose of 1 mg/kg/day after normalization for total body surface area). In humans, overdosage has been associated with vomiting, facial flushing, cheilosis, abdominal pain, headache, dizziness, and ataxia. These symptoms quickly resolve without apparent residual effects.

Isotretinoin capsules cause life-threatening birth defects at any dosage (see Boxed CONTRAINDICATIONS AND WARNINGS). Patients who can become pregnant who present with isotretinoin overdose must be evaluated for pregnancy. Patients who are pregnant should receive counseling about the risks to the fetus, as described in the Boxed CONTRAINDICATIONS AND WARNINGS. Non-pregnant patients must be warned to avoid pregnancy for at least one month and receive contraceptive counseling as described in PRECAUTIONS. Educational materials for such patients can be obtained by calling the manufacturer. Because an overdose would be expected to result in higher levels of isotretinoin in semen than found during a normal treatment course, male patients should use a condom, or avoid reproductive sexual activity with a patient who is or might become pregnant, for one month after the overdose. All patients with isotretinoin overdose should not donate blood for at least one month.

DOSAGE AND ADMINISTRATION

Isotretinoin capsules should be administered with a meal (see PRECAUTIONS: Information for Patients).

The recommended dosage range for isotretinoin capsules are 0.5 to 1 mg/kg/day given in two divided doses with food for 15 to 20 weeks. In studies comparing 0.1, 0.5, and 1 mg/kg/day^8, it was found that all dosages provided initial clearing of disease, but there was a greater need for retreatment with the lower dosages. During treatment, the dose may be adjusted according to response of the disease and/or the appearance of clinical side effects – some of which may be dose related. Adult patients whose disease is very severe with scarring or is primarily manifested on the trunk may require dose adjustments up to 2 mg/kg/day, as tolerated. Failure to take isotretinoin capsules with food will significantly decrease absorption. Before upward dose adjustments are made, the patients should be questioned about their compliance with food instructions. The safety of once daily dosing with isotretinoin capsules have not been established. Once daily dosing is notrecommended.

If the total nodule count has been reduced by more than 70% prior to completing 15 to 20 weeks of treatment, the drug may be discontinued. After a period of 2 months or more off therapy, and if warranted by persistent or recurring severe nodular acne, a second course of therapy may be initiated. The optimal interval before retreatment has not been defined for patients who have not completed skeletal growth. Long-term use of isotretinoin capsules, even in low doses, has not been studied, and is not recommended. It is important that isotretinoin capsules be given at the recommended doses for no longer than the recommended duration. The effect of long-term use of isotretinoin capsules on bone loss is unknown (see WARNINGS: Skeletal: Bone Mineral Density, Hyperostosis, and Premature Epiphyseal closure).

Contraceptive measures must be followed for any subsequent course of therapy (see PRECAUTIONS).

Table 4 Isotretinoin Dosing by Body Weight (Based on Administration With Food)
Body Weight |  | Total mg/day
kilograms | pounds | 0.5 mg/kg | 1 mg/kg | 2 mg/kg [See DOSAGE AND ADMINISTRATION: the recommended dosage range is 0.5 to 1 mg/kg/day.]
40 | 88 | 20 | 40 | 80
50 | 110 | 25 | 50 | 100
60 | 132 | 30 | 60 | 120
70 | 154 | 35 | 70 | 140
80 | 176 | 40 | 80 | 160
90 | 198 | 45 | 90 | 180
100 | 220 | 50 | 100 | 200

INFORMATION FOR PHARMACISTS

Access the iPLEDGE REMS system via the internet (www.ipledgeprogram.com), or telephone (1-866-495-0654) to obtain an authorization and the "do not dispense to patient after"date. Isotretinoin capsules must only be dispensed in no more than a 30-day supply.

REFILLS REQUIRE A NEW PRESCRIPTION AND A NEW AUTHORIZATION FROM THE iPLEDGE SYSTEM.

An isotretinoin capsules Medication Guide must be given to the patient each time isotretinoin capsules are dispensed, as required by law. This isotretinoin capsules Medication Guide is an important part of the risk management program for the patient.

HOW SUPPLIED

Soft gelatin capsules, 10 mg (pale yellow), imprinted in black ink with "V10". Boxes of 30 containing 3 Prescription Packs of 10 capsules (NDC 0832-8301-30). Boxes of 100 containing 10 Prescription Packs of 10 capsules (NDC 0832-8301-01). Soft gelatin capsules, 20 mg (white to slight pink), imprinted in black ink with "V20". Boxes of 30 containing 3 Prescription Packs of 10 capsules (NDC 0832-8302-30). Boxes of 100 containing 10 Prescription Packs of 10 capsules (NDC 0832-8302-01). Soft gelatin capsules, 30 mg (pink), imprinted in black ink with "V30". Boxes of 30 containing 3 Prescription Packs of 10 capsules (NDC 0832-8303-30). Boxes of 100 containing 10 Prescription Packs of 10 capsules (NDC 0832-8303-01). Soft gelatin capsules, 40 mg (orange), imprinted in black ink with "V40". Boxes of 30 containing 3 Prescription Packs of 10 capsules (NDC 0832-8304-30). Boxes of 100 containing 10 Prescription Packs of 10 capsules (NDC 0832-8304-01).

Storage

Store at 20° to 25°C (68° to 77°F). [See USP Controlled Room Temperature]. Protect from light.

REFERENCES

1. Peck GL, Olsen TG, Yoder FW, et al. Prolonged remissions of cystic and conglobate acne with 13- cis-retinoic acid. N Engl J Med300:329–333, 1979.
2. Pochi PE, Shalita AR, Strauss JS, Webster SB. Report of the consensus conference on acne classification. J Am Acad Dermatol24:495–500, 1991.
3. Farrell LN, Strauss JS, Stranieri AM. The treatment of severe cystic acne with 13- cis-retinoic acid: evaluation of sebum production and the clinical response in a multiple-dose trial. J Am Acad Dermatol3:602–611, 1980.
4. Jones H, Blanc D, Cunliffe WJ. 13- cis-retinoic acid and acne. Lancet2:1048–1049, 1980.
5. Katz RA, Jorgensen H, Nigra TP. Elevation of serum triglyceride levels from oral isotretinoin in disorders of keratinization. Arch Dermatol116:1369–1372, 1980.
6. Ellis CN, Madison KC, Pennes DR, Martel W, Voorhees JJ. Isotretinoin therapy is associated with early skeletal radiographic changes. J Am Acad Dermatol10:1024–1029, 1984.
7. Dicken CH, Connolly SM. Eruptive xanthomas associated with isotretinoin (13- cis-retinoic acid). Arch Dermatol116:951–952, 1980.
8. Strauss JS, Rapini RP, Shalita AR, et al. Isotretinoin therapy for acne: results of a multicenter dose-response study. J Am Acad Dermatol10:490–496, 1984.

Made in Switzerland

Distributed by
UPSHER-SMITH LABORATORIES, LLC
Maple Grove, MN 55369

All trademarks are property of their respective owners.

Revised: 3/2023

PATIENT INFORMATION

Document Patient Identification Number__________________________________

Patient Enrollment Form for Patients who can get Pregnant

To be completed by the patient (and their parent or guardian [A parent or guardian of a minor patient (under age 18) must also read and initial each item before signing the consent.] if patient is under age 18) and signed by their doctor.

Read each item below and initial in the space provided to show that you understand each item and agree to follow your doctor's instructions. Do not sign this consent and do not take isotretinoin if there is anything that you do not understand.

______________________________________________________________________________________________________________________________
(Patient's Name)

- I understand that there is a very high chance that my unborn baby could have severe birth defects if I am pregnant or become pregnant while taking isotretinoin. This can happen with any amount and even if taken for short periods of time. This is why I must not be pregnant while taking isotretinoin.
  Initial: ______
- I understand that I must not get pregnant one month before, during the entire time of my treatment, and for one month after the end of my treatment with isotretinoin.
  Initial: ______
- I understand that I must avoid having any sexual contact (penis-vaginal) with a partner who could get me pregnant completely, or I must use two separate, effective forms of birth control (contraception) at the same time. The only exceptions are if I have had surgery to remove the uterus (a hysterectomy) or both of my ovaries (bilateral oophorectomy), or my doctor has medically confirmed that I am post-menopausal.
  Initial: ______
- I understand that hormonal birth control products are among the most effective forms of birth control. Combination birth control pills and other hormonal products include skin patches, shots, under-the-skin implants, vaginal rings, and intrauterine devices (IUDs). Any method of birth control can fail. That is why I must use two different birth control forms at the same time, starting one month before, during, and for one month after stopping therapy every time I have any sexual contact (penis-vaginal) with a partner who could get me pregnant, even if one of the forms I choose is hormonal birth control.
  Initial: ______
- I understand that the following are effective forms of birth control:
  Primary forms | Secondary forms
  - tying my tubes (tubal sterilization) - male vasectomy - intrauterine device - hormonal (combination birth control pills, skin patches, shots, under-the-skin implants or vaginal ring) | Barrier:; - male latex condom with or without spermicide - diaphragm with spermicide - cervical cap with spermicide; Other:; - vaginal sponge (contains spermicide)
  A diaphragm and cervical cap must each be used with spermicide, a special cream that kills sperm.
  I understand that at least one of my two forms of birth control must be a primary form.
  Initial: ______
- I will talk with my doctor about any medicines including herbal products I plan to take during my isotretinoin treatment because hormonal birth control forms may not work if I am taking certain medicines or herbal products.
  Initial: ______
- I may receive a free birth control counseling session from a doctor or other family planning expert. My isotretinoin doctor can give me an Isotretinoin Contraception Referral Form for this freeconsultation.
  Initial: ______
- I must begin using the birth control forms I have chosen as described above at least one month before I start taking isotretinoin.
  Initial: ______
- I cannot get my first prescription for isotretinoin unless my doctor has told me that I have two negative pregnancy test results. The first pregnancy test should be done when my doctor decides to prescribe isotretinoin. The second pregnancy test must be done in a lab during the first 5 days of my menstrual period right before starting isotretinoin therapy treatment, or as instructed by my doctor. I will then have one pregnancy test; in a lab.
  - every month during treatment
  - at the end of treatment
  - and 1 month after stopping treatment
  I must not start taking isotretinoin until I am sure that I am not pregnant, have negative results from two pregnancy tests, and the second test has been done in a lab.
  Initial: ______
- I have read and understand the materials my doctor has provided to me, including the Guide for Patients who Can Get Pregnant,and the Fact Sheet on the iPLEDGE REMS.
  I have received information on emergency birth control.
  Initial: ______
- I must stop taking isotretinoin right away and call my doctor if I get pregnant, miss my expected menstrual period, stop using birth control, or have any sexual contact (penis-vaginal) with a partner who could get me pregnant without using my two birth control forms at any time.
  Initial: ______
- My doctor provided me information about the purpose and importance of providing information to the iPLEDGE REMS should I become pregnant while taking isotretinoin or within one month of the last dose. I understand that if I become pregnant, information about my pregnancy, my health, and my baby's health may be shared with the makers of isotretinoin, authorized parties who maintain the iPLEDGE REMS for the makers of isotretinoin and government health regulatory authorities.
  Initial: ______
- I understand that being qualified to receive isotretinoin in the iPLEDGE REMS means that I:
  - have had two negative urine or blood pregnancy tests before receiving the first isotretinoin prescription. The second test must be done in a lab. I must have a negative result from a urine or blood pregnancy test done in a lab repeated each month before I receive another isotretinoin prescription.
  - have chosen and agreed to use two forms of effective birth control at the same time. At least one form must be a primary form of birth control, unless I have chosen never to have any sexual contact (penis-vaginal) with a partner who could get me pregnant (abstinence), or I have undergone a hysterectomy or bilateral oophorectomy, or I have been medically confirmed to be post-menopausal. I must use two forms of birth control for at least one month before I start isotretinoin therapy, during therapy, and for one month after stopping therapy. I must receive counseling, repeated on a monthly basis, about birth control and behaviors associated with an increased risk of pregnancy.
  - have signed a Patient Enrollment Form for Patients who can get Pregnant that contains warnings about the chance of possible birth defects if I am pregnant or become pregnant and my unborn baby is exposed to isotretinoin.
  - have been informed of and understand the purpose and importance of providing information to the iPLEDGE REMS should I become pregnant while taking isotretinoin or within 1 month of the last dose.
  - have interacted with the iPLEDGE REMS before starting isotretinoin and on a monthly basis to answer questions on the program requirements and to enter my two chosen forms of birth control.
    Initial: ______

My doctor has answered all my questions about isotretinoin and I understand that it is my responsibility not to get pregnant one month before, during isotretinoin treatment, or for one month after I stop taking isotretinoin.
Initial: ______

I now authorize my doctor ________________________ to begin my treatment with isotretinoin.

Patient Signature:
_____________________________ Date: ________________________

Parent/Guardian Signature (if under age 18):
_____________________________ Date: ________________________

Please print:
Patient Name and Address_________________________________________________________
_____________________________________________________________________________
Telephone_____________________________________________________________________

I have fully explained to the patient, _______________________, the nature and purpose of the treatment described above and the risks to patients who can get pregnant. I have asked the patient if there are any questions regarding treatment with isotretinoin and have answered those questions to the best of my ability.

Doctor Signature: ___________________________________________________________________________________

Date: ______________

PLACE THE ORIGINAL SIGNED DOCUMENTS IN THE PATIENT'S MEDICAL RECORD. PLEASE PROVIDE A COPY TO THE PATIENT.

Document Patient Identification Number ___________________________________

Patient Enrollment Form for Patients who cannot get Pregnant

To be completed by patient (and parent or guardian if patient is under age 18) and signed by the doctor.

Read each item below and initial in the space provided if you understand each item and agree to follow your doctor's instructions. A parent or guardian of a patient under age 18 must also read and understand each item before signing the agreement.

Do not sign this agreement and do not take isotretinoin if there is anything that you do not understand about all the information you have received about using isotretinoin.

- I, ________________________________________________________________________,
  (Patient's Name)
  understand that isotretinoin is a medicine used to treat severe nodular acne that cannot be cleared up by any other acne treatments, including antibiotics. In severe nodular acne, many red, swollen, tender lumps form in the skin. If untreated, severe nodular acne can lead to permanent scars.
  Initials: ______
- My doctor has told me about my choices for treating my acne.
  Initials: ______
- I understand that there are serious side effects that may happen while I am taking isotretinoin. These have been explained to me. These side effects include serious birth defects in babies of pregnant patients. [Note: There is a second Patient Enrollment Form for Patients who can get Pregnant.]
  Initials: ______
- I understand that some patients, while taking isotretinoin or soon after stopping isotretinoin, have become depressed or developed other serious mental problems. Symptoms of depression include sad, "anxious" or empty mood, irritability, acting on dangerous impulses, anger, loss of pleasure or interest in social or sports activities, sleeping too much or too little, changes in weight or appetite, school or work performance going down, or trouble concentrating. Some patients taking isotretinoin have had thoughts about hurting themselves or putting an end to their own lives (suicidal thoughts). Some people tried to end their own lives. And some people have ended their own lives. There were reports that some of these people did not appear depressed. There have been reports of patients on isotretinoin becoming aggressive or violent. No one knows if isotretinoin caused these behaviors or if they would have happened even if the person did not take isotretinoin. Some people have had other signs of depression while taking isotretinoin (see # 7below).
  Initials: ______
- Before I start taking isotretinoin, I agree to tell my doctor if I have everhad symptoms of depression (see # 7below), been psychotic, attempted suicide, had any other mental problems, or take medicine for any of these problems. Being psychotic means having a loss of contact with reality, such as hearing voices or seeing things that are not there.
  Initials: ______
- Before I start taking isotretinoin, I agree to tell my doctor if, to the best of my knowledge, anyone in my family has ever had symptoms of depression, been psychotic, attempted suicide, or had any other serious mental problems.
  Initials: ______
- Once I start taking isotretinoin, I agree to stop using isotretinoin and tell my doctor right away if any of the following signs and symptoms of depression or psychosis happen. I:
  - Start to feel sad or have crying spells
  - Lose interest in activities I once enjoyed
  - Sleep too much or have trouble sleeping
  - Become more irritable, angry, or aggressive than usual (for example, temper outbursts, thoughts of violence)
  - Have a change in my appetite or body weight
  - Have trouble concentrating
  - Withdraw from my friends or family
  - Feel like I have no energy
  - Have feelings of worthlessness or guilt
  - Start having thoughts about hurting myself or taking my own life (suicidal thoughts)
  - Start acting on dangerous impulses
  - Start seeing or hearing things that are not real
  Initials: ______
- I agree to return to see my doctor every month I take isotretinoin to get a new prescription for isotretinoin, to check my progress, and to check for signs of side effects.
  Initials: ______
- Isotretinoin will be prescribed just for me – I will not share isotretinoin with other people because it may cause serious side effects, including birth defects.
  Initials: ______
- I will not give blood while taking isotretinoin or for 1 month after I stop taking isotretinoin. I understand that if someone who is pregnant gets my donated blood, their baby may be exposed to isotretinoin and may be born with serious birth defects.
  Initials: ______
- I have read the Fact Sheet for the iPLEDGE REMS,and other materials my provider provided me containing important safety information about isotretinoin. I understand all the information I received.
  Initials: ______
- My doctor and I have decided I should take isotretinoin. I understand that I must be qualified in the iPLEDGE REMS to have my prescription filled each month. I understand that I can stop taking isotretinoin at any time. I agree to tell my doctor if I stop taking isotretinoin.
  Initials: ______

I now allow my doctor ___________________________ to begin my treatment with isotretinoin.

Patient Signature:
_______________________________________ Date: ________________________

Parent/Guardian Signature (if under age 18):
_______________________________________ Date: ________________________

Patient Name (print) ____________________________________________________________________________________________________________

Patient Address _______________________________________________________________________________________________________________

Telephone (_______._______.__________)

I have:

- fully explained to the patient, _______________________________________, the nature and purpose of isotretinoin treatment, including its benefits and risks
- provided the patient with the appropriate educational materials, such as the Fact Sheet for the iPLEDGE REMS,and asked the patient if there are any questions regarding their treatment with isotretinoin
- answered those questions to the best of my ability

Doctor Signature: _______________________________________________________________________________________________________________

Date: _____________

PLACE THE ORIGINAL SIGNED DOCUMENTS IN THE PATIENT'S MEDICAL RECORD. PLEASE PROVIDE A COPY TO THE PATIENT.

MEDICATION GUIDE

Isotretinoin (eye "soe tret 'i noyn) Capsules, USP

Read the Medication Guide that comes with isotretinoin capsules before you start taking it and each time you get a prescription. There may be new information. This information does not take the place of talking with your doctor about your medical condition or your treatment.

What is the most important information I should know about isotretinoin capsules?

1. Isotretinoin capsules are used to treat a type of severe acne (nodular acne) that has not been helped by other treatments, including antibiotics.
2. Because isotretinoin capsules can cause birth defects, isotretinoin capsules are only for patients who can understand and agree to carry out all of the instructions in the iPLEDGE REMS.
3. Isotretinoin capsules may cause serious mental health problems.

1. Birth defects (deformed babies), loss of a baby before birth (miscarriage), death of the baby, and early (premature) births.Patients who are pregnant or who plan to become pregnant must not take isotretinoin capsules. Patients must not get pregnant:
  1. for 1 month before starting isotretinoin capsules
  2. while taking isotretinoin capsules
  3. for 1 month after stopping isotretinoin capsules
  If you get pregnant while taking isotretinoin capsules, stop taking it right away and call your doctor.Doctors and patients should report all cases of pregnancy to:
  1. FDA MedWatch at 1-800-FDA-1088, and
  2. The iPLEDGE pregnancy registry at 1-866-495-0654
2. Serious mental health problems.Isotretinoin capsules may cause:
  1. depression
  2. psychosis(seeing or hearing things that are not real)
  3. suicide. Some patients taking isotretinoin capsules have had thoughts about hurting themselves or putting an end to their own lives (suicidal thoughts). Some people tried to end their own lives. And some people have ended their own lives.
  Stop isotretinoin capsules and call your doctor right away if you or a family member notices that you have any of the following signs and symptoms of depression or psychosis:
  1. start to feel sad or have crying spells
  2. lose interest in activities you once enjoyed
  3. sleep too much or have trouble sleeping
  4. become more irritable, angry, or aggressive than usual (for example, temper outbursts, thoughts of violence)
  5. have a change in your appetite or body weight
  6. have trouble concentrating
  7. withdraw from your friends or family
  8. feel like you have no energy
  9. have feelings of worthlessness or guilt
  10. start having thoughts about hurting yourself or taking your own life (suicidal thoughts)
  11. start acting on dangerous impulses
  12. start seeing or hearing things that are not real

After stopping isotretinoin capsules, you may also need follow-up mental health care if you had any of these symptoms.

What are isotretinoin capsules?

Isotretinoin capsules are a medicine taken by mouth to treat the most severe form of acne (nodular acne) that cannot be cleared up by any other acne treatments, including antibiotics. Isotretinoin capsules can cause serious side effects (see " What is the most important information I should know about isotretinoin capsules?"). Isotretinoin capsules can only be:

1. prescribed by doctors that are enrolled in the iPLEDGE REMS
2. dispensed by a pharmacy that is enrolled with the iPLEDGE REMS
3. given to patients who are enrolled in the iPLEDGE REMS and agree to do everything required in the program.

What is severe nodular acne?

Severe nodular acne is when many red, swollen, tender lumps form in the skin. These can be the size of pencil erasers or larger. If untreated, nodular acne can lead to permanent scars.

Who should not take isotretinoin capsules?

1. Do not take isotretinoin capsule if you are pregnant, plan to become pregnant, or become pregnant during isotretinoin capsules treatment. Isotretinoin capsules causes life-threatening birth defects. See " What is the most important information I should know about isotretinoin capsules?"
2. Do not take isotretinoin capsules if you are allergic to anything in it.See the end of this Medication Guide for a complete list of ingredients in isotretinoin capsules.

What should I tell my doctor before taking isotretinoin capsules?

Tell your doctor if you or a family member has any of the following health conditions:

1. mental problems
2. asthma
3. liver disease
4. diabetes
5. heart disease
6. bone loss (osteoporosis) or weak bones
7. an eating problem called anorexia nervosa (where people eat too little)
8. food or medicine allergies

Tell your doctor if you are pregnant or breastfeeding. Isotretinoin capsules must not be used by patients who are pregnant or breastfeeding.

Tell your doctor about all of the medicines you take including prescription and non-prescription medicines, vitamins and herbal supplements.Isotretinoin capsules and certain other medicines can interact with each other, sometimes causing serious side effects. Especially tell your doctor if you take:

1. Vitamin A supplements.Vitamin A in high doses has many of the same side effects as isotretinoin capsules. Taking both together may increase your chance of getting side effects.
2. Tetracycline antibiotics.Tetracycline antibiotics taken with isotretinoin capsules can increase the chances of getting increased pressure in the brain.
3. Progestin-only birth control pills (mini-pills).They may not work while you take isotretinoin capsules. Ask your doctor or pharmacist if you are not sure what type you are using.
4. Dilantin (phenytoin).This medicine taken with isotretinoin capsules may weaken your bones.
5. Corticosteroid medicines.These medicines taken with isotretinoin capsules may weaken your bones
6. St. John's Wort.This herbal supplement may make birth control pills work less effectively.

These medicines should not be used with isotretinoin capsules unless your doctor tells you it is okay.

Know the medicines you take. Keep a list of them to show to your doctor and pharmacist. Do not take any new medicine without talking with your doctor.

How should I take isotretinoin capsules?

1. You must take isotretinoin capsules exactly as prescribed. You must also follow all the instructions of the iPLEDGE REMS. Before prescribing isotretinoin capsules, your doctor will:
  1. explain the iPLEDGE REMS to you
  2. have you sign the Patient Enrollment Form for Patients who cannot get Pregnant. Patients who can get pregnant must also sign another enrollment form.

You will not be prescribed isotretinoin capsules if you cannot agree to or follow all the instructions of the iPLEDGE REMS.

1. You will get no more than a 30-day supply of isotretinoin capsules at a time. This is to make sure you are following the isotretinoin capsules iPLEDGE REMS. You should talk with your doctor each month about side effects.
2. The amount of isotretinoin capsules you take has been specially chosen for you. It is based on your body weight, and may change during treatment.
3. Take isotretinoin capsules 2 times a day with a meal, unless your doctor tells you otherwise. Swallow your isotretinoin capsules whole with a full glass of liquid. Do not chew or suck on the capsule.Isotretinoin capsules can hurt the tube that connects your mouth to your stomach (esophagus) if it is not swallowed whole.
4. If you miss a dose, just skip that dose. Do nottake two doses at the same time.
5. If you take too much isotretinoin capsules or overdose, call your doctor or poison control center right away.
6. Your acne may get worse when you first start taking isotretinoin capsules. This should last only a short while. Talk with your doctor if this is a problem for you.
7. You must return to your doctor as directed to make sure you don't have signs of serious side effects. Your doctor may do blood tests to check for serious side effects from isotretinoin capsules. Patients who can get pregnant will get a pregnancy test each month.
8. Patients who can get pregnant must agree to use two separate forms of effective birth control at the same time one month before, while taking, and for one month after taking isotretinoin capsules. You must access the iPLEDGE REMS system to answer questions about the program requirements and to enter your two chosen forms of birth control.To access the iPLEDGE REMS system, go to www.ipledgeprogram.comor call 1-866-495-0654.

You must talk about effective birth control forms with your doctor or go for a free visit to talk about birth control with another doctor or family planning expert. Your doctor can arrange this freevisit, which will be paid for by the company that makes isotretinoin capsules.

If you have sex at any time without using two forms of effective birth control, get pregnant, or miss your expected period, stop using isotretinoin capsules and call your doctor right away.

What should I avoid while taking isotretinoin capsules?

1. Do not get pregnantwhile taking isotretinoin capsules and for one month after stopping isotretinoin capsules. See " What is the most important information I should know about isotretinoin capsules?"
2. Do not breast feedwhile taking isotretinoin capsules and for one month after stopping isotretinoin capsules. We do not know if isotretinoin capsules can pass through your milk and harm the baby.
3. Do not give bloodwhile you take isotretinoin capsules and for one month after stopping isotretinoin capsules. If someone who is pregnant gets your donated blood, their baby may be exposed to isotretinoin capsules and may be born with birth defects.
4. Do not take other medicines or herbal productswith isotretinoin capsules unless you talk to your doctor. See " What should I tell my doctor before taking isotretinoin capsules?"
5. Do not drive at night until you know if isotretinoin capsules have affected your vision.isotretinoin capsules may decrease your ability to see in the dark.
6. Do not have cosmetic procedures to smooth your skin, including waxing, dermabrasion, or laser procedures, while you are using isotretinoin capsules and for at least 6 months after you stop.Isotretinoin capsules can increase your chance of scarring from these procedures. Check with your doctor for advice about when you can have cosmetic procedures.
7. Avoid sunlight and ultraviolet lightsas much as possible. Tanning machines use ultraviolet lights. isotretinoin capsules may make your skin more sensitive to light.
8. Do not share isotretinoin capsules with other people.It can cause birth defects and other serious health problems.

What are the possible side effects of isotretinoin capsules?

1. Isotretinoin capsules can cause birth defects (deformed babies), loss of a baby before birth (miscarriage), death of the baby, and early (premature) births.See " What is the most important information I should know about isotretinoin capsules?"
2. Isotretinoin capsules may cause serious mental health problems.See " What is the most important information I should know about isotretinoin capsules?"
3. serious brain problems.Isotretinoin capsules can increase the pressure in your brain. This can lead to permanent loss of eyesight and, in rare cases, death. Stop taking isotretinoin capsules and call your doctor right away if you get any of these signs of increased brain pressure:
  1. bad headache
  2. blurred vision
  3. dizziness
  4. nausea or vomiting
  5. seizures (convulsions)
  6. stroke

1. skin problems.Skin rash can occur in patients taking isotretinoin capsules. In some patients a rash can be serious. Stop using isotretinoin capsules and call your doctor right away if you develop conjunctivitis (red or inflamed eyes, like "pink eye"), a rash with a fever, blisters on legs, arms or face and/or sores in your mouth, throat, nose, eyes, or if your skin begins to peel.
2. stomach area (abdomen) problems.Certain symptoms may mean that your internal organs are being damaged. These organs include the liver, pancreas, bowel (intestines), and esophagus (connection between mouth and stomach). If your organs are damaged, they may not get better even after you stop taking isotretinoin capsules. Stop taking isotretinoin capsules and call your doctor if you get:
  1. severe stomach, chest or bowel pain
  2. trouble swallowing or painful swallowing
  3. new or worsening heartburn
  4. diarrhea
  5. rectal bleeding
  6. yellowing of your skin or eyes
  7. dark urine

1. bone and muscle problems.Isotretinoin capsules may affect bones, muscles, and ligaments and cause pain in your joints or muscles. Tell your doctor if you plan hard physical activity during treatment with isotretinoin capsules. Tell your doctor if you get:
  1. back pain
  2. joint pain
  3. broken bone. Tell all healthcare providers that you take isotretinoin capsules if you break a bone.
    Stop isotretinoin capsules and call your doctor right away if you have muscle weakness. Muscle weakness with or without pain can be a sign of serious muscle damage.
    Isotretinoin capsules may stop long bone growth in teenagers who are still growing.

1. hearing problems.Stop using isotretinoin capsules and call your doctor if your hearing gets worse or if you have ringing in your ears. Your hearing loss may be permanent.
2. vision problems.Isotretinoin capsules may affect your ability to see in the dark. This condition usually clears up after you stop taking isotretinoin capsules, but it may be permanent. Other serious eye effects can occur. Stop taking isotretinoin capsules and call your doctor right away if you have any problems with your vision or dryness of the eyes that is painful or constant. If you wear contact lenses, you may have trouble wearing them while taking isotretinoin capsules and after treatment.
3. lipid (fats and cholesterol in blood) problems.Isotretinoin capsules can raise the level of fats and cholesterol in your blood. This can be a serious problem. Return to your doctor for blood tests to check your lipids and to get any needed treatment. These problems usually go away when isotretinoin capsules treatment is finished.
4. serious allergic reactions.Stop taking isotretinoin capsules and get emergency care right away if you develop hives, a swollen face or mouth, or have trouble breathing. Stop taking isotretinoin capsules and call your doctor if you get a fever, rash, or red patches or bruises on your legs.
5. blood sugar problems.Isotretinoin capsules may cause blood sugar problems including diabetes. Tell your doctor if you are very thirsty or urinate a lot.
6. decreased red and white blood cells.Call your doctor if you have trouble breathing, faint, or feel weak.
7. The common, less serious side effects of isotretinoin capsulesare dry skin, chapped lips, dry eyes, and dry nose that may lead to nosebleeds. Call your doctor if you get any side effect that bothers you or that does not go away.

These are not all of the possible side effects with isotretinoin capsules. Your doctor or pharmacist can give you more detailed information. Call your doctor for medical advice about side effects. You may report side effects to FDA at 1-800-FDA-1088 or Upsher-Smith Laboratories, LLC at 1-855-899-9180.

How should I store isotretinoin capsules?

1. Store isotretinoin capsules at 68° to 77°F (20° to 25°C). Protect from light.
2. Keep isotretinoin capsules and all medicines out of the reach of children.

General Information about Isotretinoin Capsules

Medicines are sometimes prescribed for conditions that are not mentioned in Medication Guides. Do not use isotretinoin capsules for a condition for which it was not prescribed. Do not give isotretinoin capsules to other people, even if they have the same symptoms that you have. It may harm them.

This Medication Guide summarizes the most important information about isotretinoin capsules. If you would like more information, talk with your doctor. You can ask your doctor or pharmacist for information about isotretinoin capsules that is written for health care professionals.

You can also call iPLEDGE REMS at 1-866-495-0654 or visit www.ipledgeprogram.com.

What are the ingredients in isotretinoin capsules?

Active Ingredient: Isotretinoin

Inactive Ingredients:yellow wax, butylated hydroxyanisole, edetate disodium, hydrogenated vegetable oil, tocopherol, and soybean oil. Gelatin capsules contain gelatin, glycerin, and non-crystallizing sorbitol solution, with the following dye systems: 10 mg – ferric oxide (yellow) and titanium dioxide; 20 mg - titanium dioxide; 30 mg – titanium dioxide and ferric oxide (red); 40 mg – FD&C Yellow No. 6 and titanium dioxide.

The edible imprinting ink for all the capsules contains: shellac glaze, dehydrated alcohol, isopropyl alcohol, iron oxide black, N-butyl alcohol, propylene glycol, and ammonium hydroxide.

This Medication Guide has been approved by the U.S. Food and Drug Administration.

Made in Switzerland

Distributed by
UPSHER-SMITH LABORATORIES, LLC
Maple Grove, MN 55369

All trademarks are property of their respective owners.

Revised: 3/2023

PRINCIPAL DISPLAY PANEL - 10 mg Blister Pack Box

NDC 0832-8301-30

Isotretinoin
Capsules, USP

10 mg

Each capsule contains
10 mg isotretinoin, USP.

Rx only

CAUSES
BIRTH DEFECTS

DO NOT GET
PREGNANT

30 Capsules
(3 x 10 Prescription Packs)

UPSHER-SMITH

PRINCIPAL DISPLAY PANEL - 20 mg Blister Pack Box

NDC 0832-8302-30

Isotretinoin
Capsules, USP

20 mg

Each capsule contains
20 mg isotretinoin, USP.

Rx only

CAUSES
BIRTH DEFECTS

DO NOT GET
PREGNANT

30 Capsules
(3 x 10 Prescription Packs)

UPSHER-SMITH

PRINCIPAL DISPLAY PANEL - 30 mg Blister Pack Box

NDC 0832-8303-30

Isotretinoin
Capsules, USP

30 mg

Each capsule contains
30 mg isotretinoin, USP.

Rx only

CAUSES
BIRTH DEFECTS

DO NOT GET
PREGNANT

30 Capsules
(3 x 10 Prescription Packs)

UPSHER-SMITH

PRINCIPAL DISPLAY PANEL - 40 mg Blister Pack Box

NDC 0832-8304-30

Isotretinoin
Capsules, USP

40 mg

Each capsule contains
40 mg isotretinoin, USP.

Rx only

CAUSES
BIRTH DEFECTS

DO NOT GET
PREGNANT

30 Capsules
(3 x 10 Prescription Packs)

UPSHER-SMITH